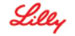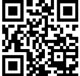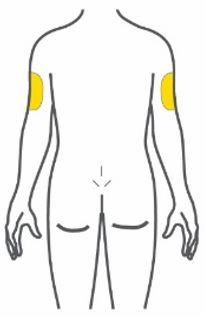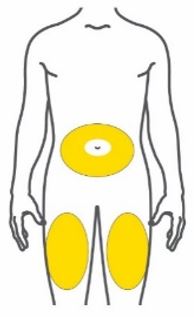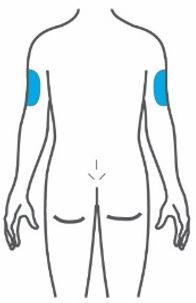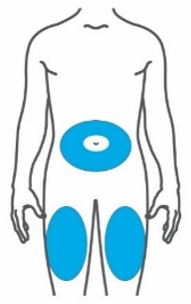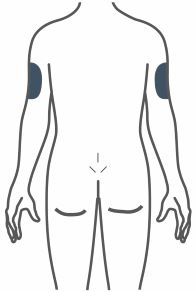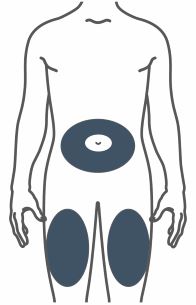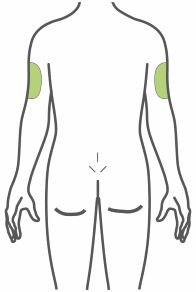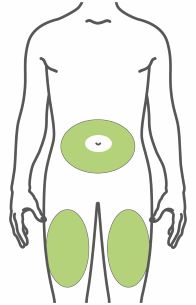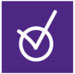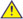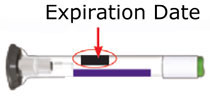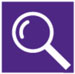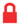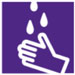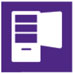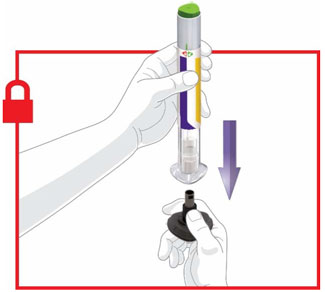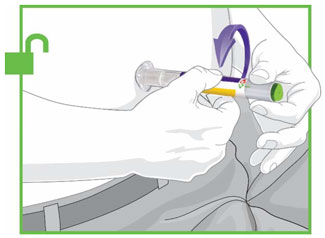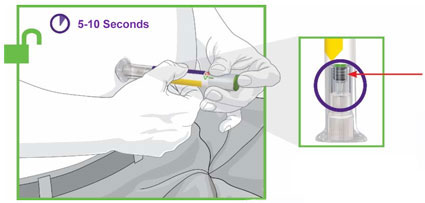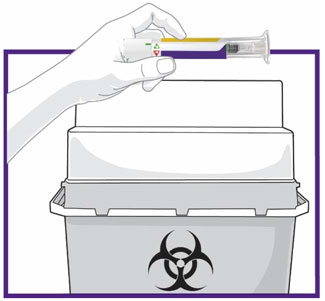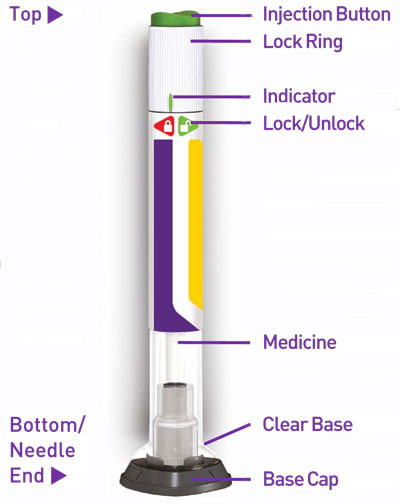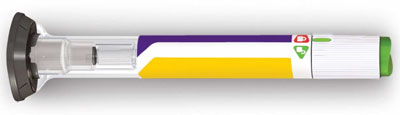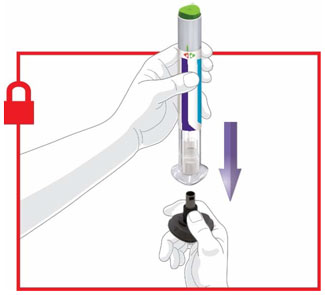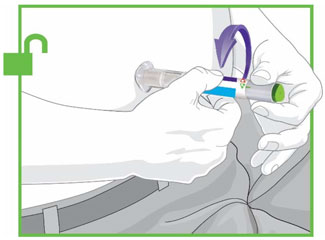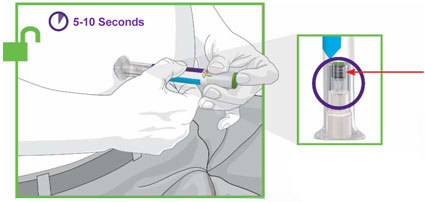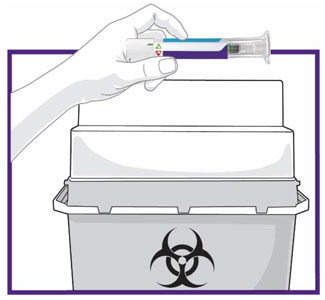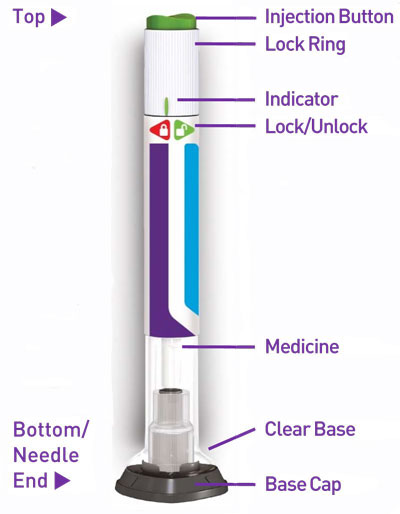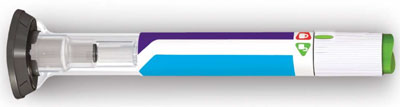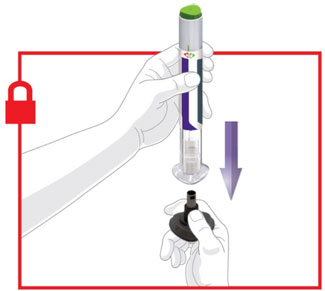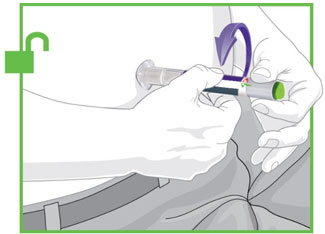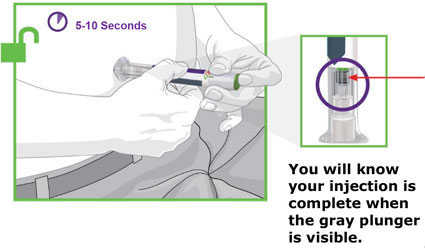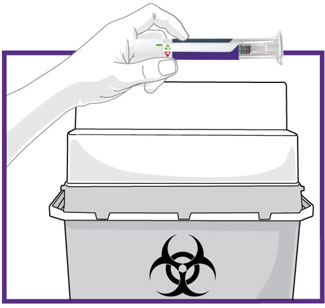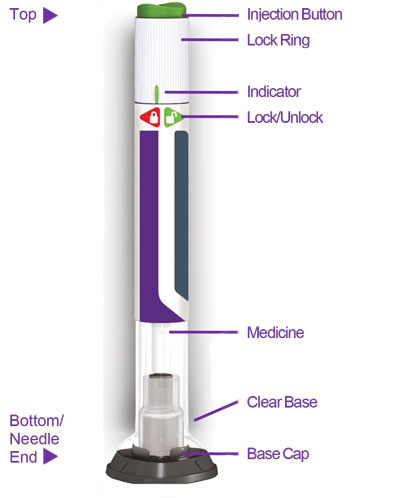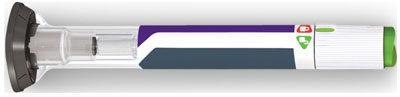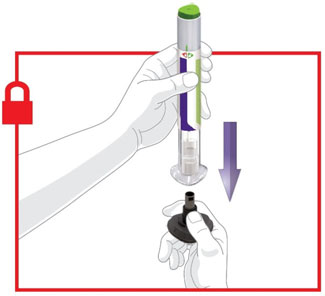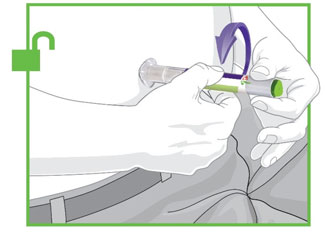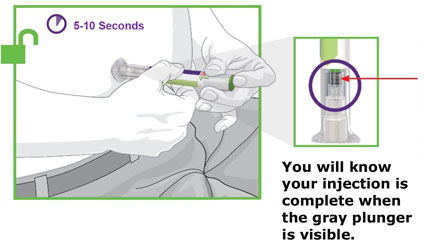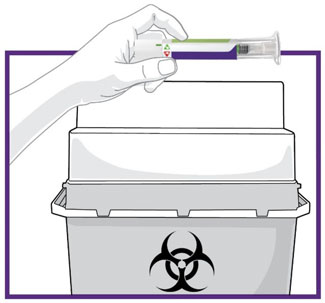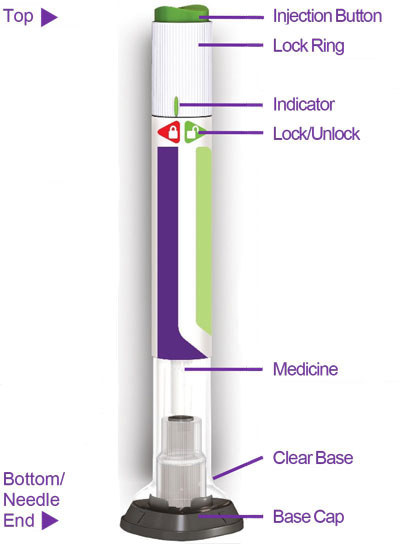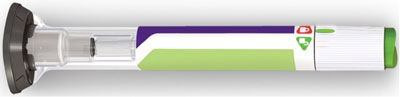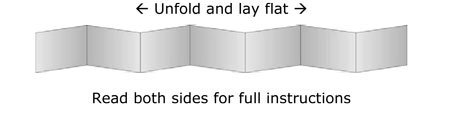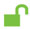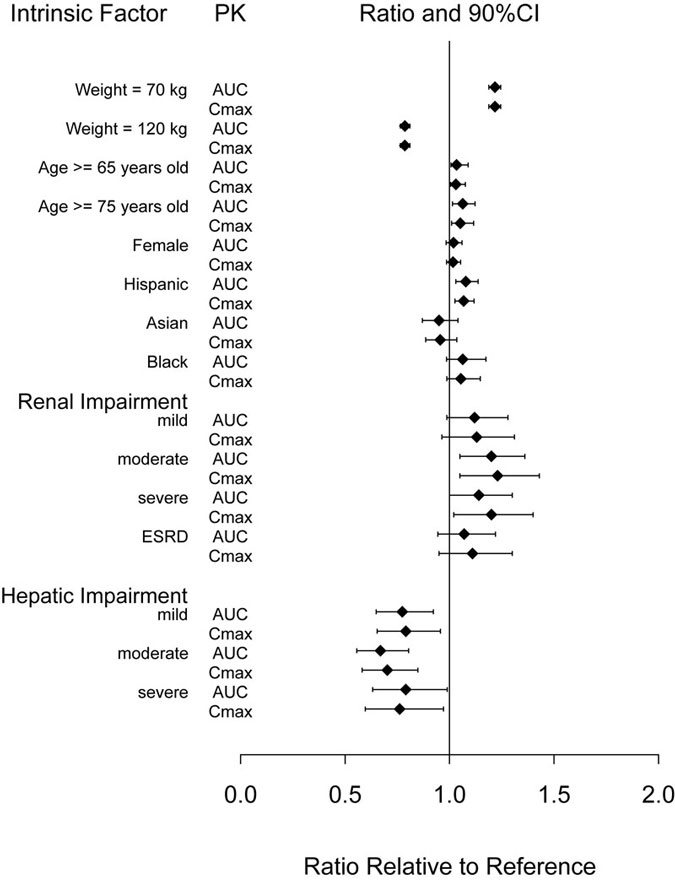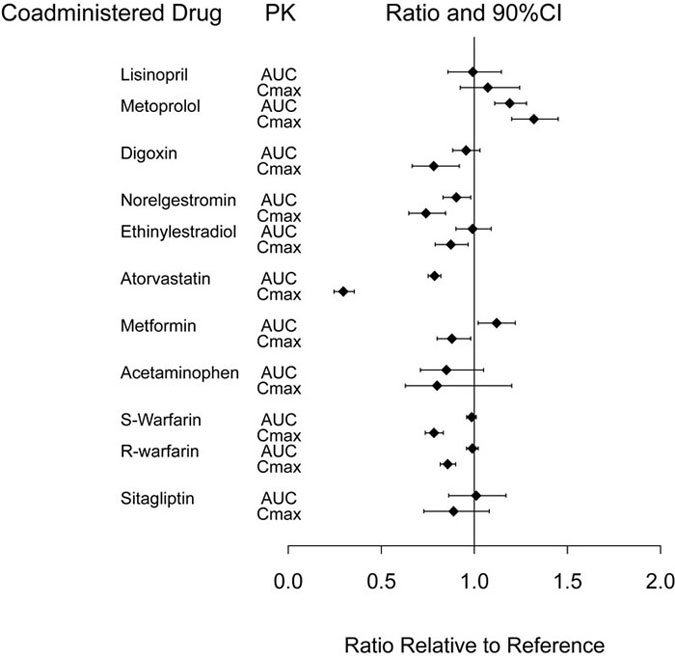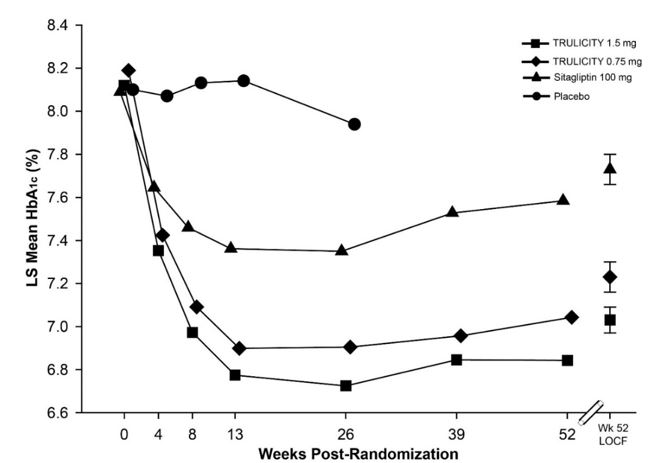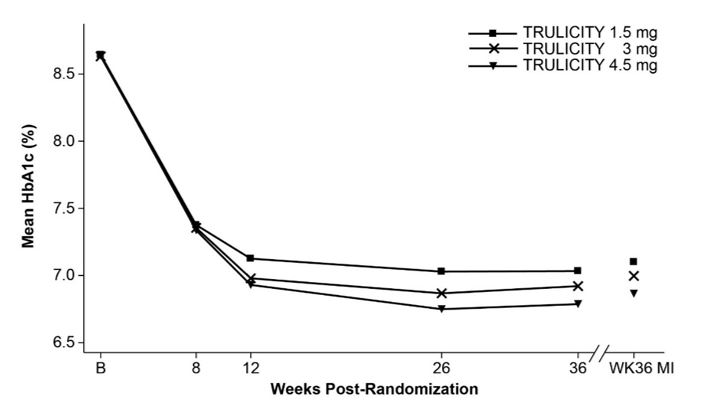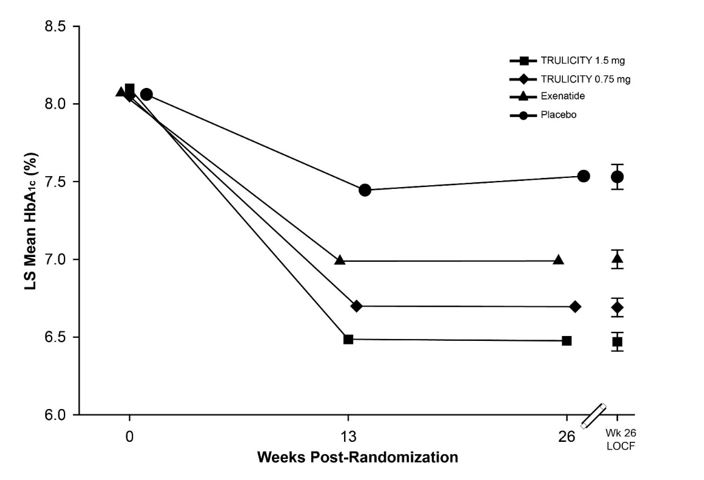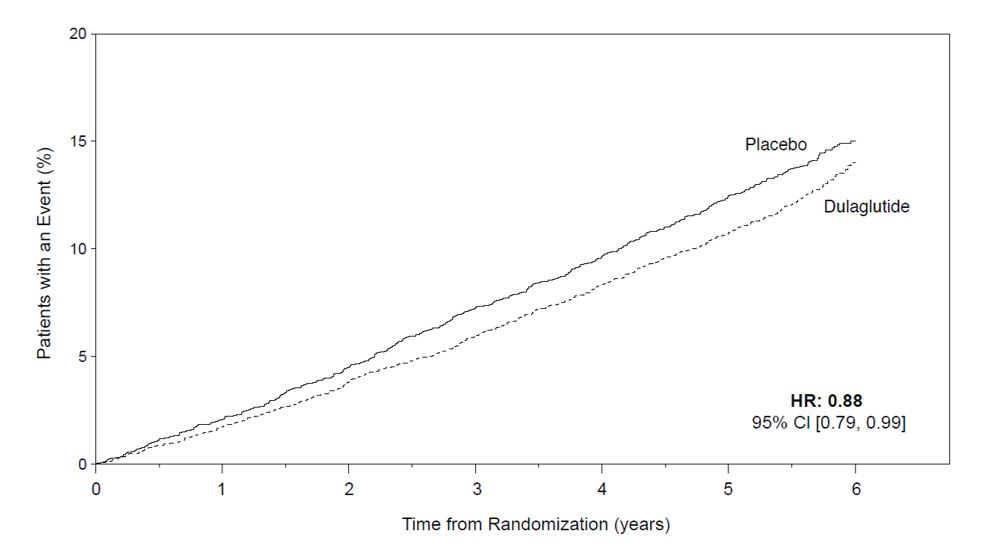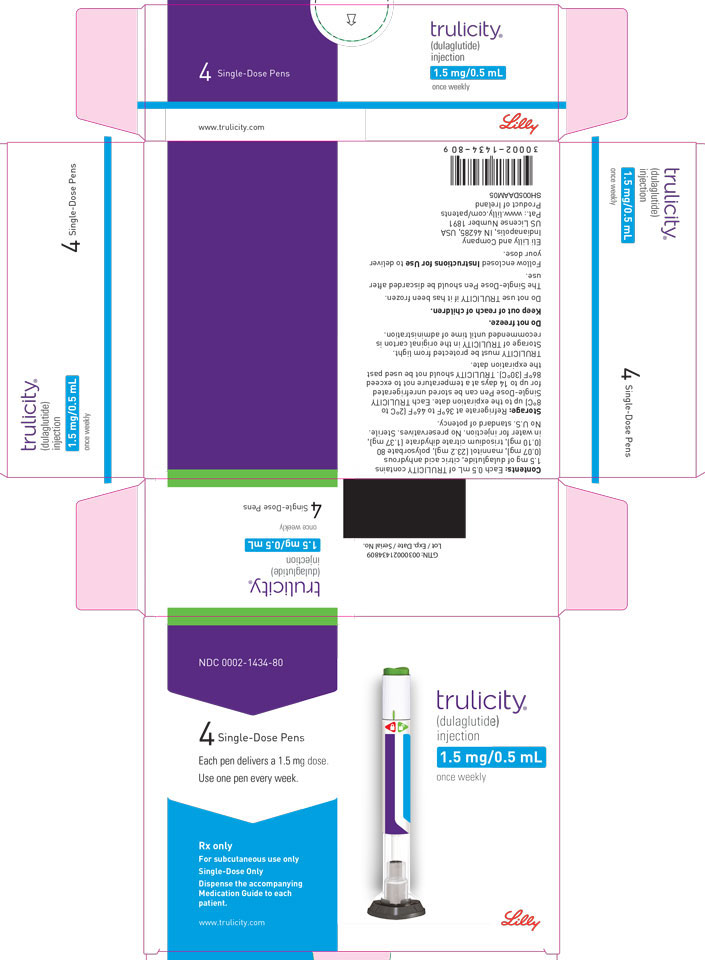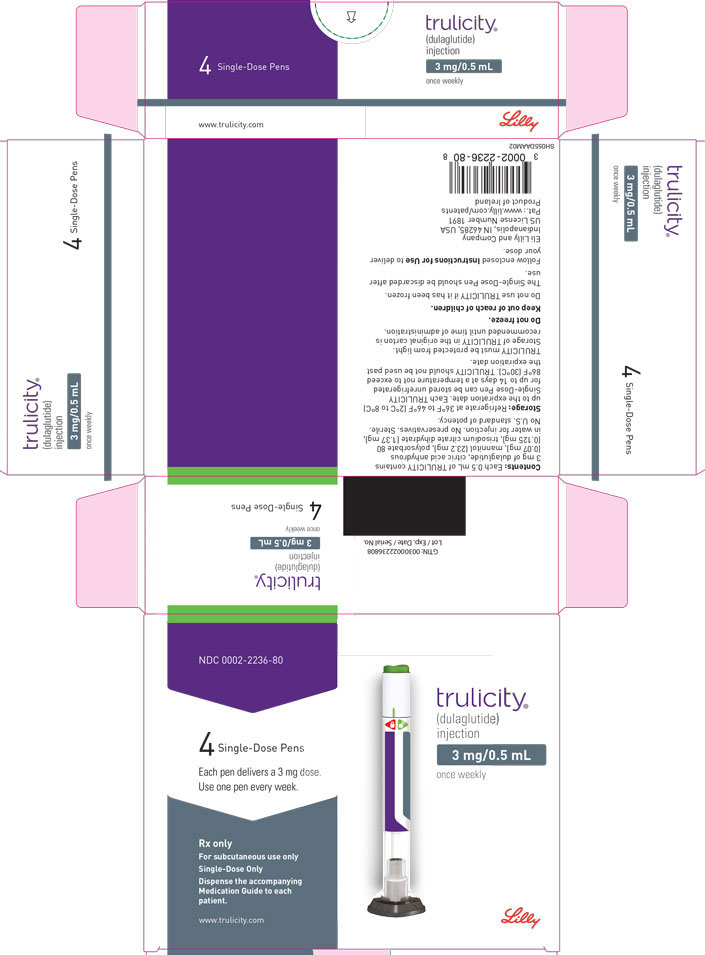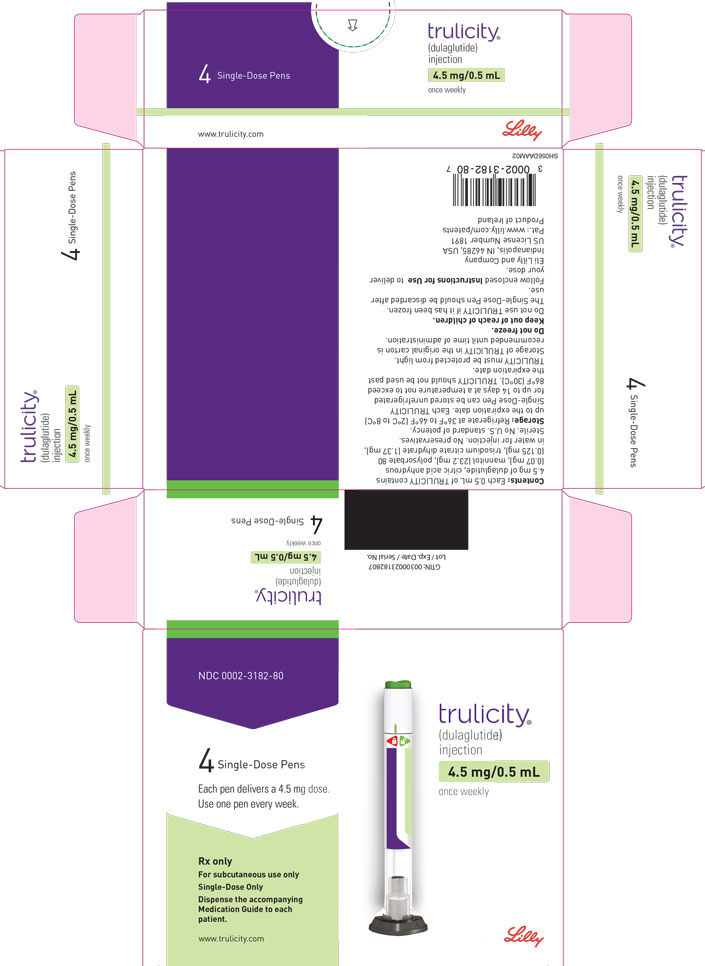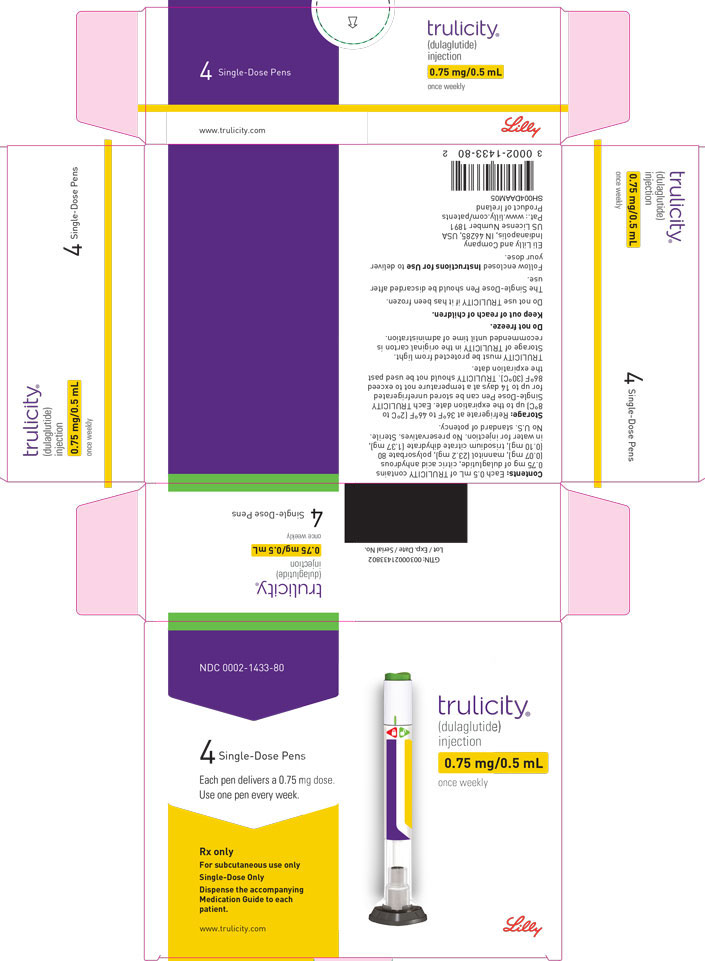 DRUG LABEL: Trulicity
NDC: 0002-1433 | Form: INJECTION, SOLUTION
Manufacturer: Eli Lilly and Company
Category: prescription | Type: HUMAN PRESCRIPTION DRUG LABEL
Date: 20251118

ACTIVE INGREDIENTS: Dulaglutide 0.75 mg/0.5 mL
INACTIVE INGREDIENTS: Trisodium Citrate Dihydrate 1.37 mg/0.5 mL; Anhydrous Citric Acid 0.07 mg/0.5 mL; Mannitol 23.2 mg/0.5 mL; Polysorbate 80 0.10 mg/0.5 mL; Water

HIGHLIGHTS OF PRESCRIBING INFORMATION

These highlights do not include all the information needed to use TRULICITY safely and effectively. See full prescribing information for TRULICITY.
TRULICITY (dulaglutide) injection, for subcutaneous use
Initial U.S. Approval: 2014

RECENT MAJOR CHANGES

Warnings and Precautions
 | Severe Gastrointestinal Adverse Reactions (5.6) | 11/2024
Warnings and Precautions
 | Pulmonary Aspiration During General Anesthesia or Deep Sedation (5.9) | 11/2024

WARNING: RISK OF THYROID C-CELL TUMORS

See full prescribing information for complete boxed warning.

- Dulaglutide causes thyroid C-cell tumors in rats. It is unknown whether TRULICITY causes thyroid C-cell tumors, including medullary thyroid carcinoma (MTC), in humans as the human relevance of dulaglutide-induced rodent thyroid C-cell tumors has not been determined (5.1, 13.1).
- TRULICITY is contraindicated in patients with a personal or family history of MTC and in patients with Multiple Endocrine Neoplasia syndrome type 2 (MEN 2). Counsel patients regarding the potential risk of MTC and symptoms of thyroid tumors (4, 5.1).

1 INDICATIONS AND USAGE

TRULICITY® is a glucagon-like peptide-1 (GLP-1) receptor agonist indicated (1):

- As an adjunct to diet and exercise to improve glycemic control in adults and pediatric patients 10 years of age and older with type 2 diabetes mellitus.
- To reduce the risk of major adverse cardiovascular events in adults with type 2 diabetes mellitus who have established cardiovascular disease or multiple cardiovascular risk factors.

2 DOSAGE AND ADMINISTRATION

Adult Dosage (2.1)

- Recommended starting dosage is 0.75 mg injected subcutaneously once weekly.
- After 4 weeks, the dosage may be increased to 1.5 mg once weekly for additional glycemic control.
- If additional glycemic control is needed, increase dosage in 1.5 mg increments after at least 4 weeks on the current dosage.
- Maximum recommended dosage is 4.5 mg injected subcutaneously once weekly.

Pediatric Dosage (2.2)

- Recommended starting dosage is 0.75 mg injected subcutaneously once weekly.
- If additional glycemic control is needed, increase dosage to the maximum recommended dosage of 1.5 mg once weekly after at least 4 weeks on the 0.75 mg dosage.

Recommendations Regarding Missed Dose (2.3)

- If a dose is missed, administer the missed dose as soon as possible if there are at least 3 days (72 hours) until the next scheduled dose.

Important Administration Instructions (2.4)

- Administer once weekly at any time of day with or without food.
- Inject subcutaneously in the abdomen, thigh, or upper arm.

3 DOSAGE FORMS AND STRENGTHS

- Injection: 0.75 mg/0.5 mL solution in a single-dose pen (3)
- Injection: 1.5 mg/0.5 mL solution in a single-dose pen (3)
- Injection: 3 mg/0.5 mL solution in a single-dose pen (3)
- Injection: 4.5 mg/0.5 mL solution in a single-dose pen (3)

4 CONTRAINDICATIONS

- Patients with a personal or family history of medullary thyroid carcinoma or in patients with Multiple Endocrine Neoplasia syndrome type 2 (4).
- Patients with a serious hypersensitivity reaction to dulaglutide or any of the product components (4).

5 WARNINGS AND PRECAUTIONS

- Thyroid C-cell Tumors: See Boxed Warning (5.1).
- Acute Pancreatitis: Has been observed in patients treated with GLP-1 receptor agonists, including TRULICITY. Discontinue if pancreatitis is suspected (5.2).
- Hypoglycemia: Concomitant use with an insulin secretagogue or insulin may increase the risk of hypoglycemia, including severe hypoglycemia. Reducing the dose of insulin secretagogue or insulin may be necessary (5.3).
- Hypersensitivity Reactions: Serious hypersensitivity reactions (e.g., anaphylactic reactions and angioedema) have occurred. Discontinue TRULICITY and promptly seek medical advice (5.4).
- Acute Kidney Injury Due to Volume Depletion: Monitor renal function in patients reporting adverse reactions that could lead to volume depletion (5.5).
- Severe Gastrointestinal Adverse Reactions: Use may be associated with gastrointestinal adverse reactions, sometimes severe. TRULICITY is not recommended in patients with severe gastroparesis (5.6).
- Diabetic Retinopathy Complications: Have been reported in a cardiovascular outcomes trial. Monitor patients with a history of diabetic retinopathy (5.7).
- Acute Gallbladder Disease: If cholelithiasis or cholecystitis are suspected, gallbladder studies are indicated (5.8).
- Pulmonary Aspiration During General Anesthesia or Deep Sedation: Has been reported in patients receiving GLP-1 receptor agonists undergoing elective surgeries or procedures. Instruct patients to inform healthcare providers of any planned surgeries or procedures (5.9).

6 ADVERSE REACTIONS

Most common adverse reactions (incidence ≥5%) are nausea, diarrhea, vomiting, abdominal pain, and decreased appetite (6.1).

To report SUSPECTED ADVERSE REACTIONS, contact Eli Lilly and Company at 1-800-LillyRx (1-800-545-5979) or FDA at 1-800-FDA-1088 or www.fda.gov/medwatch.

7 DRUG INTERACTIONS

Oral Medications: Delays gastric emptying and has the potential to reduce the rate of absorption of concomitantly administered oral medications (7.1).

8 USE IN SPECIFIC POPULATIONS

Pregnancy: Should be used during pregnancy only if the potential benefit justifies the potential risk to fetus (8.1).

FULL PRESCRIBING INFORMATION

WARNING: RISK OF THYROID C-CELL TUMORS

- In male and female rats, dulaglutide causes a dose-related and treatment-duration-dependent increase in the incidence of thyroid C-cell tumors (adenomas and carcinomas) after lifetime exposure. It is unknown whether TRULICITY causes thyroid C-cell tumors, including medullary thyroid carcinoma (MTC), in humans as human relevance of dulaglutide-induced rodent thyroid C-cell tumors has not been determined [see Warnings and Precautions (5.1), and Nonclinical Toxicology (13.1)].
- TRULICITY is contraindicated in patients with a personal or family history of MTC and in patients with Multiple Endocrine Neoplasia syndrome type 2 (MEN 2). Counsel patients regarding the potential risk of MTC with use of TRULICITY and inform them of symptoms of thyroid tumors (e.g., mass in the neck, dysphagia, dyspnea, persistent hoarseness). Routine monitoring of serum calcitonin or using thyroid ultrasound is of uncertain value for early detection of MTC in patients treated with TRULICITY [see Contraindications (4) and Warnings and Precautions (5.1)].

1 INDICATIONS AND USAGE

TRULICITY® is indicated:

- As an adjunct to diet and exercise to improve glycemic control in adults and pediatric patients 10 years of age and older with type 2 diabetes mellitus.
- To reduce the risk of major adverse cardiovascular events (cardiovascular death, non-fatal myocardial infarction, or non-fatal stroke) in adults with type 2 diabetes mellitus who have established cardiovascular disease or multiple cardiovascular risk factors.

2 DOSAGE AND ADMINISTRATION

2.1 Adult Dosage

- The recommended starting dosage of TRULICITY is 0.75 mg injected subcutaneously once weekly. Follow the dosage escalation below to reduce the risk of gastrointestinal adverse reactions [see Warnings and Precautions (5.6) and Adverse Reactions (6.1)].
- After 4 weeks, the dosage may be increased to 1.5 mg once weekly for additional glycemic control.
- If additional glycemic control is needed, increase the dosage in 1.5 mg increments after at least 4 weeks on the current dosage.
- The maximum recommended dosage is 4.5 mg injected subcutaneously once weekly.

2.2 Pediatric Dosage

- The recommended starting dosage of TRULICITY is 0.75 mg injected subcutaneously once weekly.
- If additional glycemic control is needed, increase the dosage to the maximum recommended dosage of 1.5 mg once weekly after at least 4 weeks on the 0.75 mg dosage to reduce the risk of gastrointestinal adverse reactions [see Warnings and Precautions (5.6) and Adverse Reactions (6.1)].

2.3 Recommendations Regarding Missed Dose

- If a dose is missed, instruct patients to administer the dose as soon as possible if there are at least 3 days (72 hours) until the next scheduled dose. If less than 3 days remain before the next scheduled dose, skip the missed dose and administer the next dose on the regularly scheduled day. In each case, patients can then resume their regular once weekly dosing schedule.
- The day of weekly administration can be changed, if necessary, as long as the last dose was administered 3 or more days before the new day of administration.

2.4 Important Administration Instructions

- Prior to initiation, train patients and caregivers on proper injection technique [see Instructions for Use].
- Administer TRULICITY once weekly, any time of day, with or without food.
- Inject TRULICITY subcutaneously in the abdomen, thigh, or upper arm.
- Rotate injection sites with each dose.
- Inspect TRULICITY visually before use. It should appear clear and colorless. Do not use TRULICITY if particulate matter or coloration is seen.
- When using TRULICITY with insulin, administer as separate injections and never mix. It is acceptable to inject TRULICITY and insulin in the same body region, but the injections should not be adjacent to each other.

3 DOSAGE FORMS AND STRENGTHS

Injection: TRULICITY is a clear and colorless solution available as:

- 0.75 mg/0.5 mL solution in a single-dose pen
- 1.5 mg/0.5 mL solution in a single-dose pen
- 3 mg/0.5 mL solution in a single-dose pen
- 4.5 mg/0.5 mL solution in a single-dose pen

4 CONTRAINDICATIONS

TRULICITY is contraindicated in patients with:

- Personal or family history of medullary thyroid carcinoma (MTC) or in patients with Multiple Endocrine Neoplasia syndrome type 2 (MEN 2) [see Warnings and Precautions (5.1)].
- Serious hypersensitivity reaction to dulaglutide or to any of the product components. Serious hypersensitivity reactions including anaphylactic reactions and angioedema have been reported with TRULICITY [see Warnings and Precautions (5.4)].

5 WARNINGS AND PRECAUTIONS

5.1 Risk of Thyroid C-cell Tumors

In male and female rats, dulaglutide causes a dose-related and treatment-duration-dependent increase in the incidence of thyroid C-cell tumors (adenomas and carcinomas) after lifetime exposure [see Nonclinical Toxicology (13.1)]. Glucagon-like peptide-1 (GLP-1) receptor agonists have induced thyroid C-cell adenomas and carcinomas in mice and rats at clinically relevant exposures. It is unknown whether TRULICITY will cause thyroid C-cell tumors, including medullary thyroid carcinoma (MTC), in humans, as the human relevance of dulaglutide-induced rodent thyroid C-cell tumors has not been determined.

One case of MTC was reported in a patient treated with TRULICITY in a clinical trial. This patient had pretreatment calcitonin levels approximately 8 times the upper limit of normal (ULN). An additional case of C-cell hyperplasia with elevated calcitonin levels following treatment was reported in the cardiovascular outcomes trial (REWIND). Cases of MTC in patients treated with liraglutide, another GLP-1 receptor agonist, have been reported in the postmarketing period; the data in these reports are insufficient to establish or exclude a causal relationship between MTC and GLP-1 receptor agonist use in humans.

TRULICITY is contraindicated in patients with a personal or family history of MTC or in patients with MEN 2. Counsel patients regarding the potential risk for MTC with the use of TRULICITY and inform them of symptoms of thyroid tumors (e.g. a mass in the neck, dysphagia, dyspnea, persistent hoarseness).

Routine monitoring of serum calcitonin or using thyroid ultrasound is of uncertain value for early detection of MTC in patients treated with TRULICITY. Such monitoring may increase the risk of unnecessary procedures, due to the low test specificity for serum calcitonin and a high background incidence of thyroid disease. Significantly elevated serum calcitonin values may indicate MTC and patients with MTC usually have calcitonin values >50 ng/L. If serum calcitonin is measured and found to be elevated, the patient should be further evaluated. Patients with thyroid nodules noted on physical examination or neck imaging should also be further evaluated.

5.2 Acute Pancreatitis

Acute pancreatitis, including fatal and non-fatal hemorrhagic or necrotizing pancreatitis, has been observed in patients treated with GLP-1 receptor agonists, including TRULICITY [see Adverse Reactions (6.1)].

After initiation of TRULICITY, observe patients carefully for signs and symptoms of pancreatitis (including persistent severe abdominal pain, sometimes radiating to the back, which may or may not be accompanied by vomiting). If pancreatitis is suspected, discontinue TRULICITY and initiate appropriate management.

5.3 Hypoglycemia with Concomitant Use of Insulin Secretagogues or Insulin

Patients receiving TRULICITY in combination with an insulin secretagogue (e.g., sulfonylurea) or insulin may have an increased risk of hypoglycemia, including severe hypoglycemia [see Adverse Reactions (6.1) and Drug Interactions (7)].

The risk of hypoglycemia may be lowered by a reduction in the dose of sulfonylurea (or other concomitantly administered insulin secretagogue) or insulin. Inform patients using these concomitant medications of the risk of hypoglycemia and educate them on the signs and symptoms of hypoglycemia.

5.4 Hypersensitivity Reactions

There have been postmarketing reports of serious hypersensitivity reactions including anaphylactic reactions and angioedema in patients treated with TRULICITY [see Adverse Reactions (6.2)]. If a hypersensitivity reaction occurs, discontinue TRULICITY; treat promptly per standard of care, and monitor until signs and symptoms resolve. TRULICITY is contraindicated in patients with a previous serious hypersensitivity reaction to dulaglutide or to any of the components of TRULICITY.

Anaphylaxis and angioedema have been reported with other GLP-1 receptor agonists. Use caution in a patient with a history of angioedema or anaphylaxis with another GLP-1 receptor agonist because it is unknown whether such patients will be predisposed to anaphylaxis with TRULICITY.

5.5 Acute Kidney Injury Due to Volume Depletion

There have been postmarketing reports of acute kidney injury, in some cases requiring hemodialysis, in patients treated with GLP-1 receptor agonists, including TRULICITY [see Adverse Reactions (6.2)]. The majority of the reported events occurred in patients who experienced gastrointestinal reactions leading to dehydration such as nausea, vomiting, or diarrhea [see Adverse Reactions (6.1)]. Monitor renal function in patients reporting adverse reactions to TRULICITY that could lead to volume depletion, especially during dosage initiation and escalation of TRULICITY.

5.6 Severe Gastrointestinal Adverse Reactions

Use of TRULICITY has been associated with gastrointestinal adverse reactions, sometimes severe [see Adverse Reactions (6)]. In the pool of placebo-controlled trials, severe gastrointestinal adverse reactions were reported more frequently among patients receiving TRULICITY (0.75 mg 2.2%, 1.5 mg 4.3%) than placebo (1.4%).

TRULICITY is not recommended in patients with severe gastroparesis.

5.7 Diabetic Retinopathy Complications in Patients with a History of Diabetic Retinopathy

In a cardiovascular outcomes trial with a median follow up of 5.4 years involving patients with type 2 diabetes with established cardiovascular disease or multiple cardiovascular risk factors, diabetic retinopathy complications occurred in patients treated with TRULICITY 1.5 mg (1.9%) and placebo (1.5%). These events were prospectively ascertained as a secondary composite endpoint. The proportion of patients with diabetic retinopathy complications was larger among patients with a history of diabetic retinopathy at baseline (TRULICITY 8.5%, placebo 6.2%) than among patients without a known history of diabetic retinopathy (TRULICITY 1%, placebo 1%).

Rapid improvement in glucose control has been associated with a temporary worsening of diabetic retinopathy. Patients with a history of diabetic retinopathy should be monitored for progression of diabetic retinopathy.

5.8 Acute Gallbladder Disease

Acute events of gallbladder disease such as cholelithiasis or cholecystitis have been reported in GLP-1 receptor agonist trials and postmarketing. In a cardiovascular outcomes trial with a median follow up of 5.4 years, cholelithiasis occurred at a rate of 0.62/100 patient-years in TRULICITY-treated patients and 0.56/100 patient-years in placebo-treated patients after adjusting for prior cholecystectomy. Serious events of acute cholecystitis were reported in 0.5% and 0.3% of patients on TRULICITY and placebo respectively. If cholelithiasis is suspected, gallbladder studies and appropriate clinical follow-up are indicated.

5.9 Pulmonary Aspiration During General Anesthesia or Deep Sedation

TRULICITY delays gastric emptying [see Clinical Pharmacology (12.2)]. There have been rare postmarketing reports of pulmonary aspiration in patients receiving GLP-1 receptor agonists undergoing elective surgeries or procedures requiring general anesthesia or deep sedation who had residual gastric contents despite reported adherence to preoperative fasting recommendations.

Available data are insufficient to inform recommendations to mitigate the risk of pulmonary aspiration during general anesthesia or deep sedation in patients taking TRULICITY, including whether modifying preoperative fasting recommendations or temporarily discontinuing TRULICITY could reduce the incidence of retained gastric contents. Instruct patients to inform healthcare providers prior to any planned surgeries or procedures if they are taking TRULICITY.

6 ADVERSE REACTIONS

The following serious reactions are described below or elsewhere in the prescribing information:

- Risk of Thyroid C-cell Tumors [see Warnings and Precautions (5.1)]
- Acute Pancreatitis [see Warnings and Precautions (5.2)]
- Hypoglycemia with Concomitant Use of Insulin Secretagogues or Insulin [see Warnings and Precautions (5.3)]
- Hypersensitivity Reactions [see Warnings and Precautions (5.4)]
- Acute Kidney Injury Due to Volume Depletion [see Warnings and Precautions (5.5)]
- Severe Gastrointestinal Adverse Reactions [see Warnings and Precautions (5.6)]
- Diabetic Retinopathy Complications in Patients with a History of Diabetic Retinopathy [see Warnings and Precautions (5.7)]
- Acute Gallbladder Disease [see Warnings and Precautions (5.8)]
- Pulmonary Aspiration During General Anesthesia or Deep Sedation [see Warnings and Precautions (5.9)]

6.1 Clinical Trials Experience

Because clinical studies are conducted under widely varying conditions, adverse reaction rates observed in the clinical studies of a drug cannot be directly compared to rates in the clinical studies of another drug and may not reflect the rates observed in practice.

Adverse Reactions in the Clinical Trials in Adults with Type 2 Diabetes Mellitus

Pool of Adult Placebo-Controlled Trials for TRULICITY 0.75 mg and 1.5 mg Doses

The data in Table 1 are derived from a pool of placebo-controlled trials and include 1,670 adult patients with type 2 diabetes mellitus exposed to TRULICITY with a mean duration of exposure of 23.8 weeks [see Clinical Studies (14)]. The mean age of patients was 56 years, 1% were 75 years or older and 53% were male. The population was 69% White, 7% Black or African American, 13% Asian; 30% were of Hispanic or Latino ethnicity. At baseline, the population had diabetes for an average of 8 years, a mean HbA1c of 8.0%, and 2.5% of the population reported retinopathy. Baseline estimated renal function was normal or mildly impaired (eGFR ≥60 mL/min/1.73 m^2) in 96%.

Table 1 shows adverse reactions, excluding hypoglycemia, occurring in ≥5% of TRULICITY treated adult patients and more commonly than placebo in a pool of placebo-controlled trials.

Table 1: Adverse Reactions in Pool of Placebo-Controlled Trials That Occurred in ≥5% of TRULICITY-Treated Adult Patients with Type 2 Diabetes Mellitus
Adverse Reaction | Placebo (N=568) % | TRULICITY 0.75 mg (N=836) % | TRULICITY 1.5 mg (N=834) %
Nausea | 5.3 | 12.4 | 21.1
Diarrheaa | 6.7 | 8.9 | 12.6
Vomitingb | 2.3 | 6.0 | 12.7
Abdominal Painc | 4.9 | 6.5 | 9.4
Decreased Appetite | 1.6 | 4.9 | 8.6
Dyspepsia | 2.3 | 4.1 | 5.8
Fatigued | 2.6 | 4.2 | 5.6
a Includes diarrhea, fecal volume increased, frequent bowel movements.
b Includes retching, vomiting, vomiting projectile.
c Includes abdominal discomfort, abdominal pain, abdominal pain lower, abdominal pain upper, abdominal tenderness, gastrointestinal pain.
d Includes fatigue, asthenia, malaise.
Note: Percentages reflect the number of patients that reported at least 1 treatment-emergent occurrence of the adverse reaction.

Gastrointestinal Adverse Reactions

In the pool of placebo-controlled trials, gastrointestinal (GI) adverse reactions occurred more frequently among patients who received TRULICITY compared to patients who received placebo (placebo 21%, 0.75 mg 32%, 1.5 mg 41%). A higher percentage of patients who received TRULICITY 0.75 mg (1.3%) and TRULICITY 1.5 mg (3.5%) discontinued treatment due to GI adverse reactions than patients who received placebo (0.2%). Investigators graded the severity of GI adverse reactions that occurred in those treated with 0.75 mg and 1.5 mg of TRULICITY as “mild” in 58% and 48% of cases, respectively, “moderate” in 35% and 42% of cases, respectively, or “severe” in 7% and 11% of cases, respectively.

The following GI adverse reactions were reported more frequently in TRULICITY-treated patients than placebo -treated patients (frequencies listed, respectively, as: placebo; 0.75 mg; 1.5 mg): constipation (0.7%, 3.9%, 3.7%), flatulence (1.4%, 1.4%, 3.4%), abdominal distension (0.7%, 2.9%, 2.3%), gastroesophageal reflux disease (0.5%, 1.7%, 2.0%), and eructation (0.2%, 0.6%, 1.6%).

Adult Dose Ranging Trial for TRULICITY 3 mg and 4.5 mg Doses

Table 2 shows adverse reactions occurring ≥5% in any of the treatment groups through 36 weeks in a clinical trial with 1842 adult patients with type 2 diabetes mellitus treated with TRULICITY 1.5 mg, 3 mg, or 4.5 mg subcutaneously once weekly as an add-on to metformin [see Clinical Studies (14.3)]. The adverse reaction profile is consistent with previous clinical trials in adults.

Table 2: Adverse Reactions That Occurred in ≥5% of TRULICITY-treated Adult Patients with Type 2 Diabetes Mellitus in a Clinical Trial through 36 Weeksa
Adverse Reaction | TRULICITY 1.5 mg (N=612) % | TRULICITY 3 mg (N=616) % | TRULICITY 4.5 mg (N=614) %
Nausea | 13.4 | 15.6 | 16.4
Diarrhea | 7.0 | 11.4 | 10.7
Vomiting | 5.6 | 8.3 | 9.3
Dyspepsia | 2.8 | 5.0 | 2.6
a Percentages reflect the number of patients that reported at least 1 treatment-emergent occurrence of the adverse reaction.

Other Adverse Reactions in Adults

Hypoglycemia

Table 3 summarizes the incidence of hypoglycemia in the placebo-controlled clinical studies in adult patients with type 2 diabetes mellitus: episodes with a glucose level <54 mg/dL with or without symptoms, and severe hypoglycemia, defined as an episode requiring the assistance of another person to actively administer carbohydrate, glucagon, or other resuscitative actions.

Table 3: Incidence (%) of Hypoglycemia in Adult Patients with Type 2 Diabetes Mellitus in Placebo-Controlled Trials
 | Placebo | TRULICITY 0.75 mg | TRULICITY 1.5 mg
Add-on to Metformin
(26 weeks) | N=177 | N=302 | N=304
Hypoglycemia with a glucose level <54 mg/dL | 0 | 0.3 | 0.7
Severe hypoglycemia | 0 | 0 | 0
Add-on to Metformin + Pioglitazone
(26 weeks) | N=141 | N=280 | N=279
Hypoglycemia with a glucose level <54 mg/dL | 1.4 | 2.1 | 0
Severe hypoglycemia | 0 | 0 | 0
Add-on to Glimepiride
(24 weeks) | N=60 | - | N=239
Hypoglycemia with a glucose level <54 mg/dL | 0 | - | 3.3
Severe hypoglycemia | 0 | - | 0
In Combination with Insulin Glargine ± Metformin
(28 weeks) | N=150 | - | N=150
Hypoglycemia with a glucose level <54 mg/dL | 9.3 | - | 14.7
Severe hypoglycemia | 0 | - | 0.7
Add-on to SGLT2i ± Metformin
(24 weeks) | N=140 | N=141 | N=142
Hypoglycemia with a glucose level <54 mg/dL | 0.7 | 0.7 | 0.7
Severe hypoglycemia | 0 | 0.7 | 0

Hypoglycemia was more frequent when TRULICITY was used in combination with a sulfonylurea or insulin than when used with non-secretagogues. In a 78-week adult clinical trial, hypoglycemia (glucose level <54 mg/dL) occurred in 20% and 21% of patients when TRULICITY 0.75 mg and 1.5 mg, respectively, were co-administered with a sulfonylurea. Severe hypoglycemia occurred in 0% and 0.7% of patients when TRULICITY 0.75 mg and 1.5 mg, respectively, were co-administered with a sulfonylurea. In a 52-week adult clinical trial, hypoglycemia (glucose level <54 mg/dL) occurred in 77% and 69% of patients when TRULICITY 0.75 mg and 1.5 mg, respectively, were co-administered with prandial insulin. Severe hypoglycemia occurred in 2.7% and 3.4% of patients when TRULICITY 0.75 mg and 1.5 mg, respectively, were co-administered with prandial insulin. Refer to Table 3 for the incidence of hypoglycemia in patients treated in combination with basal insulin glargine.

In the clinical trial with adult patients on TRULICITY 1.5 mg, TRULICITY 3 mg, or TRULICITY 4.5 mg once weekly, as add-on to metformin, incidences of hypoglycemia (glucose level <54 mg/dL) through 36 weeks were 1.1%, 0.3%, and 1.1%, respectively, and incidences of severe hypoglycemia were 0.2%, 0%, and 0.2%, respectively.

Cholelithiasis and Cholecystitis

In a cardiovascular outcomes trial in adult patients with type 2 diabetes mellitus and established cardiovascular (CV) disease or multiple cardiovascular risk factors with a median follow up of 5.4 years [see Clinical Studies 14.5], cholelithiasis occurred at a rate of 0.62/100 patient-years in TRULICITY-treated patients and 0.56/100 patient-years in placebo-treated patients after adjusting for prior cholecystectomy. Serious events of acute cholecystitis were reported in 0.5% and 0.3% of patients on TRULICITY and placebo respectively.

Heart Rate Increase and Tachycardia-Related Adverse Reactions

In adult patients, TRULICITY 0.75 mg and 1.5 mg resulted in a mean increase in heart rate (HR) of 2-4 beats per minute (bpm).

Adverse reactions of sinus tachycardia were reported more frequently in patients exposed to TRULICITY. Sinus tachycardia was reported in 3.0%, 2.8%, and 5.6% of patients treated with placebo, TRULICITY 0.75 mg and TRULICITY 1.5 mg, respectively. Persistence of sinus tachycardia (reported at more than 2 visits) was reported in 0.2%, 0.4% and 1.6% of patients treated with placebo, TRULICITY 0.75 mg and TRULICITY 1.5 mg, respectively. Episodes of sinus tachycardia, associated with a concomitant increase from baseline in heart rate of ≥15 beats per minute, were reported in 0.7%, 1.3% and 2.2% of patients treated with placebo, TRULICITY 0.75 mg and TRULICITY 1.5 mg, respectively.

Hypersensitivity

Systemic hypersensitivity adverse reactions, sometimes severe (e.g., severe urticaria, systemic rash, facial edema, lip swelling), occurred in 0.5% of adult patients on TRULICITY in clinical studies.

Injection-site Reactions

In the placebo-controlled studies in adults, injection-site reactions (e.g., injection-site rash, erythema) were reported in 0.5% of TRULICITY-treated patients and in 0.0% of placebo-treated patients.

PR Interval Prolongation and Adverse Reactions of First-Degree Atrioventricular (AV) Block

A mean increase from baseline in PR interval of 2-3 milliseconds was observed in TRULICITY-treated adult patients in contrast to a mean decrease of 0.9 milliseconds in placebo-treated patients. The adverse reaction of first-degree AV block occurred more frequently in patients treated with TRULICITY than placebo (0.9%, 1.7% and 2.3% for placebo, TRULICITY 0.75 mg and TRULICITY 1.5 mg, respectively). On electrocardiograms, a PR interval increase to at least 220 milliseconds was observed in 0.7%, 2.5% and 3.2% of patients treated with placebo, TRULICITY 0.75 mg and TRULICITY 1.5 mg, respectively.

Acute Pancreatitis

In a pooled analysis from the original registration studies, 12 (3.4 cases per 1,000 patient years) pancreatitis-related adverse reactions were reported in patients exposed to TRULICITY versus 3 in non-incretin comparators (2.7 cases per 1000 patient years). An analysis of adjudicated events revealed 5 cases of confirmed pancreatitis in patients exposed to TRULICITY (1.4 cases per 1,000 patient years) versus 1 case in non-incretin comparators (0.88 cases per 1,000 patient years).

Based on an analysis of adjudicated events in a clinical trial evaluating Trulicity 1.5 mg, 3 mg, or 4.5 mg once weekly, pancreatitis occurred in 1 patient exposed to TRULICITY 1.5 mg (0.2%), in 2 patients exposed to TRULICITY 3 mg (0.3%), and 3 patients exposed to TRULICITY 4.5 mg (0.5%).

Amylase and Lipase Increase

Adult patients exposed to TRULICITY had mean increases from baseline in lipase and/or pancreatic amylase of 14% to 20%, while placebo-treated patients had mean increases of up to 3%.

Adverse Reactions in the Clinical Trial of Pediatric Patients 10 Years of Age and Older with Type 2 Diabetes Mellitus

TRULICITY was administered to 150 pediatric patients 10 years of age and older with type 2 diabetes mellitus for a mean duration of 41.3 weeks [see Clinical Studies (14.6)]. The mean age was 14.5 years and 71% of patients were female. Overall, 55% were White, 15% were Black or African American, 12% were Asian, 10% were American Indian or Alaska Native, 5% were other races, and 3% had unknown race. Additionally, 55% were Hispanic or Latino, 42% were not Hispanic or Latino, and 3% had unknown ethnicity. At baseline, the mean duration of type 2 diabetes mellitus was 2 years, mean HbA1c was 8.1%, mean weight was 90.5 kg and mean BMI was 34.1 kg/m^2.

The safety profile in pediatric patients treated with TRULICITY 0.75 mg and 1.5 mg subcutaneously once-weekly was consistent with that described above for adult patients with type 2 diabetes mellitus with the exception of injection site reactions. In pediatric patients, the incidence of injection site reactions was 3.9% (2 patients) in the TRULICITY 0.75 mg group, 3.8% (2 patients) in the TRULICITY 1.5 mg group, and 2.0% (1 patient) in the placebo group.

6.2 Postmarketing Experience

The following additional adverse reactions have been reported during post-approval use of TRULICITY. Because these events are reported voluntarily from a population of uncertain size, it is generally not possible to reliably estimate their frequency or establish a causal relationship to drug exposure.

- Gastrointestinal: acute pancreatitis, hemorrhagic and necrotizing pancreatitis sometimes resulting in death, ileus
- Hepatobiliary: cholecystitis, cholelithiasis requiring cholecystectomy, cholestasis, elevation of liver enzymes, hepatitis
- Hypersensitivity: anaphylactic reactions, angioedema
- Neurologic: dysgeusia, dysesthesia
- Pulmonary: Pulmonary aspiration has occurred in patients receiving GLP-1 receptor agonists undergoing elective surgeries or procedures requiring general anesthesia or deep sedation
- Renal: acute renal failure or worsening of chronic renal failure, sometimes requiring hemodialysis
- Skin and Subcutaneous Tissue: alopecia

7 DRUG INTERACTIONS

7.1 Oral Medications

TRULICITY delays gastric emptying and thus has the potential to reduce the rate of absorption of concomitantly administered oral medications. The delay in gastric emptying is dose-dependent but is attenuated with the recommended dose escalation to higher doses of TRULICITY [see Dosage and Administration (2.1)]. The delay is largest after the first dose and diminishes with subsequent doses. In clinical pharmacology studies, TRULICITY 1.5 mg did not affect the absorption of the tested orally administered medications to a clinically relevant degree [see Clinical Pharmacology (12.3)]. There is limited experience with the use of concomitant medications in clinical trials with TRULICITY doses of 3 mg and 4.5 mg.

Monitor drug levels of oral medications with a narrow therapeutic index (e.g., warfarin) when concomitantly administered with TRULICITY.

7.2 Concomitant Use with an Insulin Secretagogue (e.g., Sulfonylurea) or with Insulin

When initiating TRULICITY, consider reducing the dose of concomitantly administered insulin secretagogues (such as sulfonylureas) or insulin to reduce the risk of hypoglycemia [see Warnings and Precautions (5.3) and Adverse Reactions (6.1)].

8 USE IN SPECIFIC POPULATIONS

8.1 Pregnancy

Risk Summary

Limited data with TRULICITY in pregnant women are not sufficient to determine a drug-associated risk for major birth defects and miscarriage. There are clinical considerations regarding the risks of poorly controlled diabetes in pregnancy [see Clinical Considerations]. Based on animal reproduction studies, there may be risks to the fetus from exposure to dulaglutide during pregnancy. TRULICITY should be used during pregnancy only if the potential benefit justifies the potential risk to the fetus.

In pregnant rats administered dulaglutide during organogenesis, early embryonic deaths, fetal growth reductions, and fetal abnormalities occurred at systemic exposures at least 6-times human exposure at the maximum recommended human dose (MRHD) of 4.5 mg/week. In pregnant rabbits administered dulaglutide during organogenesis, major fetal abnormalities occurred at 5-times human exposure at the MRHD. Adverse embryo/fetal effects in animals occurred in association with decreased maternal weight and food consumption attributed to the pharmacology of dulaglutide [see Data].

The estimated background risk of major birth defects is 6–10% in women with pre-gestational diabetes with an HbA1c >7% and has been reported to be as high as 20–25% in women with an HbA1c >10%. The estimated background risk of miscarriage for the indicated population is unknown. In the U.S. general population, the estimated background risk of major birth defects and miscarriage in clinically recognized pregnancies is 2–4% and 15–20%, respectively.

Clinical Considerations

Disease-associated maternal and/or embryo/fetal risk

Poorly controlled diabetes in pregnancy increases the maternal risk for diabetic ketoacidosis, pre-eclampsia, spontaneous abortions, preterm delivery and delivery complications. Poorly controlled diabetes increases the fetal risk for major birth defects, stillbirth, and macrosomia-related morbidity.

Data

Animal Data

Pregnant rats given subcutaneous doses of 0.49, 1.63, or 4.89 mg/kg dulaglutide every 3 days during organogenesis had systemic exposures 2-, 6-, and 18-times human exposure at the maximum recommended human dose (MRHD) of 4.5 mg/week, respectively, based on plasma area under the time-concentration curve (AUC) comparison. Reduced fetal weights associated with decreased maternal food intake and decreased weight gain attributed to the pharmacology of dulaglutide were observed at ≥1.63 mg/kg. Irregular skeletal ossifications and increases in post-implantation loss also were observed at 4.89 mg/kg.

In pregnant rabbits given subcutaneous doses of 0.04, 0.12, or 0.41 mg/kg dulaglutide every 3 days during organogenesis, systemic exposures in pregnant rabbits were 0.5-, 2-, and 5-times human exposure at the MRHD, based on plasma AUC comparison. Fetal visceral malformation of lung lobular agenesis and skeletal malformations of the vertebrae and/or ribs were observed in conjunction with decreased maternal food intake and decreased weight gain attributed to the pharmacology of dulaglutide at 0.41 mg/kg.

In a prenatal-postnatal study in F0 maternal rats given subcutaneous doses of 0.2, 0.49, or 1.63 mg/kg every third day from implantation through lactation, systemic exposures in pregnant rats were 1-, 2-, and 7-times human exposure at the MRHD, based on plasma AUC comparison. F1 pups from F0 maternal rats given 1.63 mg/kg dulaglutide had statistically significantly lower mean body weight from birth through postnatal day 63 for males and postnatal day 84 for females. F1 offspring from F0 maternal rats receiving 1.63 mg/kg dulaglutide had decreased forelimb and hindlimb grip strength and males had delayed balano-preputial separation. Females had decreased startle response. These physical findings may relate to the decreased size of the offspring relative to controls as they appeared at early postnatal assessments but were not observed at a later assessment. F1 female offspring of the F0 maternal rats given 1.63 mg/kg of dulaglutide had a longer mean escape time and a higher mean number of errors relative to concurrent control during 1 of 2 trials in the memory evaluation portion of the Biel water maze. These findings occurred in conjunction with decreased F0 maternal food intake and decreased weight gain attributed to the pharmacologic activity at 1.63 mg/kg. The human relevance of these memory deficits in the F1 female rats is not known.

8.2 Lactation

Risk Summary

There are no data on the presence of dulaglutide in human milk, the effects on the breastfed infant, or the effects on milk production. The presence of dulaglutide in milk of treated lactating animals was not determined. The developmental and health benefits of breastfeeding should be considered along with the mother's clinical need for TRULICITY and any potential adverse effects on the breastfed infant from TRULICITY or from the underlying maternal condition.

8.4 Pediatric Use

The safety and effectiveness of TRULICITY as an adjunct to diet and exercise to improve glycemic control in pediatric patients 10 years of age and older with type 2 diabetes mellitus have been established. Use of TRULICITY for this indication is supported by a 26-week, multicenter, randomized, double-blind, parallel arm, placebo-controlled trial in 154 pediatric patients 10 years of age and older with type 2 diabetes mellitus [see Clinical Studies (14.6)].

TRULICITY-treated pediatric patients reported a higher incidence of injection site-related reactions compared to TRULICITY-treated adults [see Adverse Reactions (6.1)].

The safety and effectiveness of TRULICITY have not been established in pediatric patients less than 10 years of age.

8.5 Geriatric Use

In the adult glycemic control trials [see Clinical Studies (14.2, 14.3)], 620 (19%) of TRULICITY-treated patients were 65 years of age or older and 65 (2%) of TRULICITY-treated patients were 75 years of age or older at baseline. In the TRULICITY 1.5 mg treatment arm of the REWIND trial (cardiovascular outcomes trial in adults with type 2 diabetes mellitus and cardiovascular disease or multiple cardiovascular risk factors) [see Clinical Studies (14.5)], 2,619 (53%) patients were 65 years of age or older, and 484 (10%) patients were 75 years of age or older at baseline.

No overall differences in safety or effectiveness for TRULICITY have been observed between patients 65 years of age and older and younger adult patients.

8.6 Renal Impairment

TRULICITY has been studied in patients with varying degrees of renal function, including a dedicated clinical trial in patients with moderate to severe chronic kidney disease. No overall differences in safety or effectiveness were observed in these studies according to renal function [see Clinical Studies (14.2, 14.3, 14.4)].

In a clinical pharmacology study in patients with renal impairment, including end-stage renal disease (ESRD), no clinically relevant change in dulaglutide pharmacokinetics (PK) was observed. In the 52-week trial in patients with type 2 diabetes and moderate to severe renal impairment, the PK behavior of TRULICITY 0.75 mg and 1.5 mg once weekly was similar to that demonstrated in previous clinical studies [see Clinical Pharmacology (12.3)].

No dose adjustment is recommended in patients with renal impairment including end-stage renal disease (ESRD). Monitor renal function in patients with renal impairment reporting severe adverse gastrointestinal reactions. Use TRULICITY with caution in patients with ESRD [see Warning and Precautions (5.5), Clinical Pharmacology (12.3)].

8.7 Hepatic Impairment

In a clinical pharmacology study in patients with varying degrees of hepatic impairment, no clinically relevant change in dulaglutide PK was observed [see Clinical Pharmacology (12.3)]. However, there is limited clinical experience in patients with mild, moderate, or severe hepatic impairment; therefore, use TRULICITY with caution in these patient populations.

10 OVERDOSAGE

Overdoses have been reported in clinical studies. Effects associated with these overdoses were primarily mild or moderate gastrointestinal events (e.g., nausea, vomiting) and non-severe hypoglycemia. In the event of overdose, consider contacting the Poison Help line (1-800-222-1222) or a medical toxicologist for additional overdosage management recommendations. Initiate appropriate supportive care (including frequent plasma glucose monitoring) according to the patient's clinical signs and symptoms.

11 DESCRIPTION

Dulaglutide is a human GLP-1 receptor agonist. The molecule is a fusion protein that consists of 2 identical, disulfide-linked chains, each containing an N-terminal GLP-1 analog sequence covalently linked to the Fc portion of a modified human immunoglobulin G4 (IgG4) heavy chain by a small peptide linker and is produced using mammalian cell (Chinese hamster ovary) culture. The GLP-1 analog portion of dulaglutide is 90% homologous to native human GLP-1 (7-37). Structural modifications were introduced in the GLP-1 part of the molecule responsible for interaction with the enzyme dipeptidyl-peptidase-IV (DPP-4). Additional modifications were made in an area with a potential T-cell epitope and in the areas of the IgG4 Fc part of the molecule responsible for binding the high-affinity Fc receptors and half-antibody formation. The overall molecular weight of dulaglutide is approximately 63 kilodaltons.

TRULICITY (dulaglutide) injection is a clear, colorless, sterile, preservative-free solution for subcutaneous use. Each single-dose pen contains a 0.5 mL solution of 0.75 mg, 1.5 mg, 3 mg, or 4.5 mg of dulaglutide and the following excipients: citric acid anhydrous (0.07 mg), mannitol (23.2 mg), polysorbate 80 (0.10 mg for 0.75 mg and 1.5 mg; 0.125 mg for 3 mg and 4.5 mg), and trisodium citrate dihydrate (1.37 mg), in water for injection.

12 CLINICAL PHARMACOLOGY

12.1 Mechanism of Action

TRULICITY contains dulaglutide, which is a human GLP-1 receptor agonist with 90% amino acid sequence homology to endogenous human GLP-1 (7-37). Dulaglutide activates the GLP-1 receptor, a membrane-bound cell-surface receptor coupled to adenylyl cyclase in pancreatic beta cells. Dulaglutide increases intracellular cyclic AMP (cAMP) in beta cells leading to glucose-dependent insulin release. Dulaglutide also decreases glucagon secretion and slows gastric emptying.

12.2 Pharmacodynamics

TRULICITY lowers fasting glucose and reduces postprandial glucose (PPG) concentrations in patients with type 2 diabetes mellitus. The reduction in fasting and postprandial glucose can be observed after a single dose.

Fasting and Postprandial Glucose

In a clinical pharmacology study in patients with type 2 diabetes mellitus, treatment with once weekly TRULICITY resulted in a reduction of fasting and 2-hour PPG concentrations, and postprandial serum glucose incremental AUC, when compared to placebo (-25.6 mg/dL, -59.5 mg/dL, and -197 mg*h/dL, respectively); these effects were sustained after 6 weeks of dosing with the 1.5 mg dose.

First- and Second-Phase Insulin Secretion

Both first- and second-phase insulin secretion were increased in patients with type 2 diabetes treated with TRULICITY compared with placebo.

Insulin and Glucagon Secretion

TRULICITY stimulates glucose-dependent insulin secretion and reduces glucagon secretion. Treatment with TRULICITY 0.75 mg and 1.5 mg once weekly increased fasting insulin from baseline at Week 26 by 35.38 and 17.50 pmol/L, respectively, and C-peptide concentration by 0.09 and 0.07 nmol/L, respectively, in a monotherapy trial. In the same trial, fasting glucagon concentration was reduced by 1.71 and 2.05 pmol/L from baseline with TRULICITY 0.75 mg and 1.5 mg, respectively.

Gastric Motility

Dulaglutide causes a delay of gastric emptying. The delay in gastric emptying is dose-dependent but is attenuated with adequate dose escalation to higher doses of TRULICITY. The delay is largest after the first dose and diminishes with subsequent doses.

Cardiac Electrophysiology (QTc)

The effect of dulaglutide on cardiac repolarization was tested in a thorough QTc study. Dulaglutide did not produce QTc prolongation at doses of 4 and 7 mg. The maximum recommended dose is 4.5 mg once weekly.

12.3 Pharmacokinetics

The pharmacokinetics of dulaglutide is similar between healthy subjects and patients with type 2 diabetes mellitus. Following subcutaneous administration, the time to maximum plasma concentration of dulaglutide at steady state ranges from 24 to 72 hours, with a median of 48 hours. After reaching steady state, the accumulation ratio was approximately 1.56. Steady-state plasma dulaglutide concentrations were achieved between 2 and 4 weeks following once weekly administration. Site of subcutaneous administration (abdomen, upper arm, and thigh) had no statistically significant effect on the exposure to dulaglutide.

Absorption – The mean absolute bioavailability of dulaglutide following subcutaneous administration of single 0.75 mg and 1.5 mg doses was 65% and 47%, respectively. Absolute subcutaneous bioavailability for 3 mg and 4.5 mg doses were estimated to be similar to 1.5 mg although this has not been specifically studied. Dulaglutide concentrations increased approximately proportional to dose from 0.75 mg to 4.5 mg.

Distribution – Apparent population mean central volume of distribution was 3.09 L and the apparent population mean peripheral volume of distribution was 5.98 L.

Elimination

The apparent population mean clearance of dulaglutide was 0.142 L/h. The elimination half-life of dulaglutide was approximately 5 days.

Metabolism – Dulaglutide is presumed to be degraded into its component amino acids by general protein catabolism pathways.

Specific Populations

The intrinsic factors of age (≥ 65 years), sex, race, ethnicity, body weight, or renal or hepatic impairment did not have a clinically relevant effect on the PK of dulaglutide as shown in Figure 1.

Abbreviations: AUC = area under the time-concentration curve; CI = confidence interval; Cmax = maximum concentration; ESRD = end-stage renal disease; PK = pharmacokinetics.

Note: Reference values for weight, age, gender, and race comparisons are 93 kg, 56 years old, male, and white, respectively; reference groups for renal and hepatic impairment data are subjects with normal renal and hepatic function from the respective clinical pharmacology studies. The weight values shown in the plot (70 and 120 kg) are the 10th and 90th percentiles of weight in the PK population.

Figure 1: Impact of intrinsic factors on dulaglutide pharmacokinetics.

Pediatric Patients

A population pharmacokinetic analysis was conducted for dulaglutide 0.75 mg and 1.5 mg using data from 128 pediatric patients 10 years of age and older with type 2 diabetes mellitus. The AUC in pediatric patients was approximately 37% lower than that in adult patients. However, this difference was not determined to be clinically meaningful.

Patients with Renal Impairment

Dulaglutide systemic exposure was increased by 20, 28, 14 and 12% for mild, moderate, severe, and ESRD renal impairment sub-groups, respectively, compared to subjects with normal renal function. The corresponding values for increase in Cmax were 13, 23, 20 and 11%, respectively (Figure 1). Additionally, in a 52 week clinical trial in patients with type 2 diabetes mellitus and moderate to severe renal impairment, the PK behavior of TRULICITY 0.75 mg and 1.5 mg once weekly was similar to that demonstrated in previous clinical studies [see Warning and Precautions (5.5), Use in Specific Populations (8.6)].

Patients with Hepatic Impairment

Dulaglutide systemic exposure decreased by 23, 33 and 21% for mild, moderate and severe hepatic impairment groups, respectively, compared to subjects with normal hepatic function, and Cmax was decreased by a similar magnitude (Figure 1) [see Use in Specific Populations (8.7)].

Drug Interaction Studies

The potential effect of co-administered medications on the PK of dulaglutide 1.5 mg and vice versa was studied in several single- and multiple-dose studies in healthy subjects, patients with type 2 diabetes mellitus, and patients with hypertension.

Potential for Dulaglutide to Influence the Pharmacokinetics of Other Drugs

Dulaglutide slows gastric emptying and, as a result, may reduce the extent and rate of absorption of orally co-administered medications. In clinical pharmacology studies, dulaglutide at a dose of 1.5 mg did not affect the absorption of the tested orally administered medications to any clinically relevant degree. The delay in gastric emptying is dose-dependent but is attenuated with the recommended dose escalation to higher doses of TRULICITY [see Dosage and Administration (2.1), Drug Interactions (7.1)]. The delay is largest after the first dose and diminishes with subsequent doses. PK measures indicating the magnitude of these interactions are presented in Figure 2.

Abbreviations: AUC = area under the time-concentration curve; CI = confidence interval; Cmax = maximum concentration; PK = pharmacokinetics.

Note: Reference group is co-administered medication given alone.

Figure 2: Impact of dulaglutide 1.5 mg on the pharmacokinetics of co-administered medications.

Potential for Co-administered Drugs to Influence the Pharmacokinetics of Dulaglutide

In a clinical pharmacology study, the co-administration of a single dose of 1.5 mg dulaglutide with steady-state dose of 100 mg sitagliptin caused an increase in dulaglutide AUC and Cmax of approximately 38% and 27%, which is not considered clinically relevant.

12.6 Immunogenicity

The observed incidence of anti-drug antibodies is highly dependent on the sensitivity and specificity of the assay. Differences in assay methods preclude meaningful comparisons of the incidence of anti-drug antibodies in the studies described below with the incidence of anti-drug antibodies in other studies.

In glycemic control trials in adults with type 2 diabetes mellitus (monotherapy and combination therapy) [see Clinical Studies (14.2, 14.3)], during a treatment period ranging from 24 to 104 weeks, 64/3,907 (1.6%) of TRULICITY-treated patients developed anti-dulaglutide antibodies (referred to as anti-drug-antibodies (ADA)). Of the 64 TRULICITY-treated patients that developed ADA, 34 patients (0.9% of the overall population) developed dulaglutide-neutralizing antibodies, and 36 patients (0.9% of the overall population) developed antibodies against native GLP-1. There was no identified clinically significant effect of ADA on pharmacokinetics, pharmacodynamics, safety, or effectiveness of TRULICITY over the 24 to 104 week treatment duration in the trials in adults with type 2 diabetes mellitus.

During the 26-week controlled period of the glycemic control trial in pediatric patients 10 years of age or older with type 2 diabetes mellitus [see Clinical Studies (14.6)], 4/101 (4%) of TRULICITY-treated pediatric patients developed ADA. Of the 4 pediatric patients that developed ADA, 1 patient (1% of the overall population) developed dulaglutide-neutralizing antibodies and 3 patients (3% of the overall population) developed antibodies against native GLP-1. During the 52-week postbaseline period of the same trial (through safety follow-up), 6/103 (6%) of TRULICITY-treated patients developed ADA. Of the 6 patients that developed ADA, 1 patient (1% of the overall population) developed dulaglutide-neutralizing antibodies and 4 patients (4% of the overall population) developed antibodies against native GLP-1. Because of the low occurrence of ADA, the effect of these antibodies on the pharmacokinetics, pharmacodynamics, safety, and/or effectiveness of TRULICITY is unknown in pediatric patients.

13 NONCLINICAL TOXICOLOGY

13.1 Carcinogenesis, Mutagenesis, and Impairment of Fertility

A 2-year carcinogenicity study was conducted with dulaglutide in male and female rats at doses of 0.05, 0.5, 1.5, and 5 mg/kg (0.2-, 3-, 8-, and 24-fold the MRHD of 4.5 mg once weekly based on AUC) administered by subcutaneous injection twice weekly. In rats, dulaglutide caused a dose-related and treatment-duration-dependent increase in the incidence of thyroid C-cell tumors (adenomas and/or carcinomas) compared to controls, at ≥3-fold the MRHD based on AUC. A statistically significant increase in C-cell adenomas was observed in rats receiving dulaglutide at ≥0.5 mg/kg. Numerical increases in thyroid C-cell carcinomas occurred at 5 mg/kg (24 times the MRHD based on AUC) and were considered to be treatment-related despite the absence of statistical significance.

A 6-month carcinogenicity study was conducted with dulaglutide in rasH2 transgenic mice at doses of 0.3, 1, and 3 mg/kg administered by subcutaneous injection twice weekly. Dulaglutide did not produce increased incidences of thyroid C-cell hyperplasia or neoplasia at any dose.

Dulaglutide is a recombinant protein; no genotoxicity studies have been conducted.

Human relevance of thyroid C-cell tumors in rats is unknown and could not be determined by clinical studies or nonclinical studies [see Boxed Warning and Warnings and Precautions (5.1)].

In fertility and early embryonic development studies in male and female rats, no adverse effects of dulaglutide on sperm morphology, mating, fertility, conception, and embryonic survival were observed at up to 16.3 mg/kg (55-fold the MRHD based on AUC). In female rats, an increase in the number of females with prolonged diestrus and a dose-related decrease in the mean number of corpora lutea, implantation sites, and viable embryos were observed at ≥4.9 mg/kg (≥13-fold the MRHD based on AUC), which occurred in the presence of decreased maternal food consumption and body weight gain.

13.2 Animal Toxicology and/or Pharmacology

Zucker diabetic fatty (ZDF) rats were given 0.5, 1.5, or 5 mg/kg/twice weekly of dulaglutide (1-, 3-, and 13-fold the MRHD based on AUC) for 3 months. Increases of 12% to 33% in total and pancreatic amylase, but not lipase, were observed at all doses without microscopic pancreatic inflammatory correlates in individual animals. Other changes in the dulaglutide-treated animals included increased interlobular ductal epithelium without active ductal cell proliferation (≥0.5 mg/kg), increased acinar atrophy with/without inflammation (≥1.5 mg/kg), and increased neutrophilic inflammation of the acinar pancreas (5 mg/kg).

Treatment of monkeys for 12 months with 8.15 mg/kg/twice weekly of dulaglutide (nearly 200-fold the MRHD based on AUC) demonstrated no evidence of pancreatic inflammation or pancreatic intraepithelial neoplasia. In 4 of 19 monkeys on dulaglutide treatment, there was an increase in goblet cells within the pancreatic ducts, but no differences from the control group in total amylase or lipase at study termination. There were no proliferative changes in the thyroid C-cells.

14 CLINICAL STUDIES

14.1 Overview of Clinical Trials

TRULICITY has been studied in adults as monotherapy and in combination with metformin, sulfonylurea, metformin and sulfonylurea, metformin and thiazolidinedione, sodium-glucose co-transporter-2 inhibitors (SGLT2i) with or without metformin, basal insulin with or without metformin, and prandial insulin with or without metformin. TRULICITY has also been studied in patients with type 2 diabetes mellitus and moderate to severe renal impairment.

Dose escalation was performed in one trial in adults with TRULICITY doses up to 4.5 mg added to metformin. All other clinical studies in adults evaluated TRULICITY 0.75 mg and 1.5 mg without dose escalation; patients were initiated and maintained on either 0.75 mg or 1.5 mg for the duration of the trials [see Clinical Studies (14.2, 14.3, 14.4)].

TRULICITY 0.75 mg and 1.5 mg was studied in pediatric patients 10 years of age and older with type 2 diabetes in combination with or without metformin and/or basal insulin treatment [see Clinical Studies (14.6)].

In patients with type 2 diabetes mellitus, TRULICITY produced reductions from baseline in HbA1c compared to placebo. No overall differences in glycemic effectiveness were observed across demographic subgroups (age, gender, race/ethnicity, duration of diabetes).

A cardiovascular outcomes trial was conducted in adult patients with type 2 diabetes mellitus and established cardiovascular (CV) disease or multiple cardiovascular risk factors. Patients were randomized to TRULICITY 1.5 mg or placebo both added to standard of care. TRULICITY significantly reduced the risk of first occurrence of primary composite endpoint of CV death, non-fatal MI, or non-fatal stroke [see Clinical Studies (14.5)].

14.2 Glycemic Control Monotherapy Trials in Adults with Type 2 Diabetes Mellitus

In a double-blind trial with primary endpoint at 26 weeks, 807 adult patients inadequately treated with diet and exercise, or with diet and exercise and one antidiabetic agent used at submaximal dose, were randomized to TRULICITY 0.75 mg once weekly, TRULICITY 1.5 mg once weekly, or metformin 1500 to 2000 mg/day following a two-week washout. Seventy-five percent (75%) of the randomized population were treated with one antidiabetic agent at the screening visit. Most patients previously treated with an antidiabetic agent were receiving metformin (~90%) at a median dose of 1000 mg daily and approximately 10% were receiving a sulfonylurea.

Patients had a mean age of 56 years and a mean duration of type 2 diabetes of 3 years. Forty-four percent were male. The White, Black and Asian race accounted for 74%, 7% and 8% of the population, respectively. Twenty-nine percent of the trial population were from the US.

Treatment with TRULICITY 0.75 mg and 1.5 mg once weekly resulted in reduction in HbA1c from baseline at 26-weeks (Table 4). The difference in observed effect size between TRULICITY 0.75 mg and 1.5 mg, respectively, and metformin excluded the pre-specified non-inferiority margin of 0.4%.

Table 4: Results at Week 26 in a Trial of TRULICITY as Monotherapy in Adult Patients with Type 2 Diabetes Mellitusa
 | 26-Week Primary Time Point
 | TRULICITY 0.75 mg | TRULICITY 1.5 mg | Metformin 1500-2000 mg
Intent-to-Treat (ITT) Population (N)‡ | 270 | 269 | 268
HbA1c (%) (Mean)
Baseline | 7.6 | 7.6 | 7.6
Change from baselineb | -0.7 | -0.8 | -0.6
Fasting Serum Glucose (mg/dL) (Mean)
Baseline | 161 | 164 | 161
Change from baselineb | -26 | -29 | -24
Body Weight (kg) (Mean)
Baseline | 91.8 | 92.7 | 92.4
Change from baselineb | -1.4 | -2.3 | -2.2
Abbreviation: HbA1c = hemoglobin A1c.
a Intent-to-treat population. Last observation carried forward (LOCF) was used to impute missing data. Data post-onset of rescue therapy are treated as missing. At Week 26, primary efficacy was missing for 10%, 12% and 14% of individuals randomized to TRULICITY 0.75 mg, TRULICITY 1.5 mg and metformin, respectively.
b Least-squares mean adjusted for baseline value and other stratification factors.
‡ Patients included in the analysis are a subset of the ITT population that had at least one post-baseline assessment. The primary analysis included 265 individuals in each of the treatment arms.

14.3 Glycemic Control Combination Therapy Trials in Adults with Type 2 Diabetes Mellitus

Sitagliptin-Controlled Trial (Add-on to Metformin)

In this placebo-controlled, double-blind trial with primary endpoint at 52 weeks, 972 adult patients were randomized to placebo, TRULICITY 0.75 mg once weekly, TRULICITY 1.5 mg once weekly, or sitagliptin 100 mg/day (after 26 weeks, patients in the placebo treatment group received blinded sitagliptin 100 mg/day for the remainder of the trial), all as add-on to metformin. Randomization occurred after an 11-week lead-in period to allow for a metformin titration period, followed by a 6-week glycemic stabilization period. Patients had a mean age of 54 years; mean duration of type 2 diabetes of 7 years; 48% were male; race: White, Black and Asian were 53%, 4% and 27%, respectively; and 24% of the trial population were in the US.

At the 26-week placebo-controlled time point, the HbA1c change was 0.1%, -1.0%, -1.2%, and -0.6% for placebo, TRULICITY 0.75 mg, TRULICITY 1.5 mg, and sitagliptin, respectively. The percentage of patients who achieved HbA1c <7.0% was 22%, 56%, 62% and 39% for placebo, TRULICITY 0.75 mg, TRULICITY 1.5 mg, and sitagliptin, respectively. At 26 weeks, there was a mean weight reduction of 1.4 kg, 2.7 kg, 3.0 kg, and 1.4 kg for placebo, TRULICITY 0.75 mg, TRULICITY 1.5 mg, and sitagliptin, respectively. There was a mean reduction of fasting glucose of 9 mg/dL, 35 mg/dL, 41 mg/dL, and 18 mg/dL for placebo, TRULICITY 0.75 mg, TRULICITY 1.5 mg, and sitagliptin, respectively.

Treatment with TRULICITY 0.75 mg and 1.5 mg once weekly resulted in a statistically significant reduction in HbA1c compared to placebo (at 26 weeks) and compared to sitagliptin (at 26 and 52 weeks), all in combination with metformin (Table 5 and Figure 3).

Table 5: Results at Week 52 of TRULICITY Compared to Sitagliptin used as Add-On to Metformin in Adult Patients with Type 2 Diabetes Mellitusa
 | 52-Week Primary Time Point
 | TRULICITY 0.75 mg | TRULICITY 1.5 mg | Sitagliptin 100 mg
Intent-to-Treat (ITT) Population (N)‡ | 281 | 279 | 273
HbA1c (%) (Mean)
Baseline | 8.2 | 8.1 | 8.0
Change from baselineb | -0.9 | -1.1 | -0.4
Difference from sitagliptinb (95% CI) | -0.5 (-0.7, -0.3)†† | -0.7 (-0.9, -0.5)†† | -
Percentage of patients HbA1c <7.0% | 49## | 59## | 33
Fasting Plasma Glucose (mg/dL) (Mean)
Baseline | 174 | 173 | 171
Change from baselineb | -30 | -41 | -14
Difference from sitagliptinb (95% CI) | -15 (-22, -9) | -27 (-33, -20) | -
Body Weight (kg) (Mean)
Baseline | 85.5 | 86.5 | 85.8
Change from baselineb | -2.7 | -3.1 | -1.5
Difference from sitagliptinb (95% CI) | -1.2 (-1.8, -0.6) | -1.5 (-2.1, -0.9) | -
Abbreviations: HbA1c = hemoglobin A1c.
a All ITT patients randomized after the dose-finding portion of the trial. Last observation carried forward (LOCF) was used to impute missing data. At Week 52 primary efficacy was missing for 15%, 19%, and 20% of individuals randomized to TRULICITY 0.75 mg, TRULICITY 1.5 mg and sitagliptin, respectively.
b Least-squares (LS) mean adjusted for baseline value and other stratification factors.
‡ Patients included in the analysis are a subset of the ITT population that had at least one post-baseline assessment. The primary analysis included 276, 277, and 270 individuals randomized to TRULICITY 0.75 mg, TRULICITY 1.5 mg and sitagliptin, respectively.
†† Multiplicity adjusted 1-sided p-value <0.001, for superiority of TRULICITY compared to sitagliptin, assessed only for HbA1c.
## p<0.001 TRULICITY compared to sitagliptin, assessed only for HbA1c <7.0%.

Number of patients with observed data
Placebo | 139 | 108
TRULICITY 0.75 mg | 281 | 258 | 238
TRULICITY 1.5 mg | 279 | 249 | 225
Sitagliptin | 273 | 241 | 219
Mean HbA1c adjusted for baseline HbA1c and country.

Figure 3: Adjusted Mean HbA1c at each Time Point (ITT, MMRM) and at Week 52 (ITT, LOCF) in Adult Patients with Type 2 Diabetes Mellitus

Dosage Ranging Trial of TRULICITY 1.5, 3 mg, and 4.5 mg (Add-on to Metformin)

In this parallel-arm, double-blind trial with primary endpoint at 36 weeks, a total of 1842 adult patients were randomized 1:1:1 to TRULICITY 1.5 mg, TRULICITY 3 mg, or TRULICITY 4.5 mg once weekly, all as add-on to metformin (NCT03495102).

Following randomization, all patients received TRULICITY 0.75 mg once weekly. The dose was increased every 4 weeks to the next higher dose until the patients reached their assigned dose (1.5 mg, 3 mg, or 4.5 mg). Patients were to remain on the assigned study dose for the duration of the trial.

Patients had a mean age of 57.1 years; a mean duration of type 2 diabetes of 7.6 years; 51.2% were male; race: White, Black, and Asian were 85.8%, 4.5%, and 2.4%, respectively; and 27.6% of the trial population was in the US.

At 36 weeks, treatment with TRULICITY 4.5 mg resulted in a statistically significant reduction in HbA1c and in body weight compared to TRULICITY 1.5 mg (Table 6 and Figure 4).

Table 6. Results at Week 36 of TRULICITY 1.5 mg Compared to 3 mg and 4.5 mg as Add-On to Metformin in Adult Patients with Type 2 Diabetes Mellitusa
 | 36-Week Primary Time Point
 | TRULICITY 1.5 mg | TRULICITY 3 mg | TRULICITY 4.5 mg
Intent-to-Treat (ITT) Population (N) | 612 | 616 | 614
HbA1c (%) (Mean)
Baseline | 8.6 | 8.6 | 8.6
Change from baselineb | -1.5 | -1.6 | -1.8
Difference from 1.5 mgb (95% CI) |  | -0.1 (-0.2, 0.0) | -0.2 (-0.4, -0.1) ^
Percentage of patients HbA1c <7.0% c | 50 | 56 | 62
Fasting Serum Glucose (mg/dL) (Mean)
Baseline | 185 | 184 | 183
Change from baselineb | -45 | -46 | -51
Difference from 1.5 mgb (95% CI) |  | - 2 (-7, 3) | -6 (-11, -2)
Body Weight (kg) (Mean)
Baseline | 95.5 | 96.3 | 95.4
Change from baselineb | -3.0 | -3.8 | -4.6
Difference from 1.5 mgb (95% CI) |  | -0.9 (-1.4, -0.4) | -1.6 (-2.2, -1.1) ^^
Abbreviations: HbA1c = hemoglobin A1c
a Intent-to-treat population. At Week 36, primary efficacy was missing for 7%, 7%, and 6% of individuals treated with TRULICITY 1.5 mg, TRULICITY 3 mg, and TRULICITY 4.5 mg, respectively.
b Least-squares mean adjusted for baseline value and other stratification factors. Missing data were imputed using multiple imputation.
c Patients with missing HbA1c data at Week 36 were considered as not achieving HbA1c target.
^ p=0.0001 for superiority compared to TRULICITY 1.5 mg, overall type I error controlled.
^^ p<0.0001 for superiority compared to TRULICITY 1.5 mg, overall type I error controlled.

Number of patients with observed data
TRULICITY 1.5 mg | 612 |  | 567
TRULICITY 3 mg | 616 |  | 572
TRULICITY 4.5 mg | 614 |  | 575

Observed mean HbA1c at scheduled visits and retrieved dropout multiple imputation (MI) based estimate at week 36.

Figure 4: Mean HbA1c at each Time Point (ITT) and at Week 36 (ITT, MI)

Placebo-Controlled Trial (Add-on to Sulfonylurea)

In this 24-week placebo-controlled, double-blind trial, 299 adult patients were randomized to and received placebo or once weekly TRULICITY 1.5 mg, both as add-on to glimepiride. Patients had a mean age of 58 years; mean duration of type 2 diabetes of 8 years; 44% were male; race: White, Black, and Asian were 83%, 4%, and 2%, respectively; and 24% of the trial population were in the US.

At 24 weeks, treatment with once weekly TRULICITY 1.5 mg resulted in a statistically significant reduction in HbA1c compared to placebo (Table 7).

Table 7: Results at Week 24 of TRULICITY Compared to Placebo as Add-On to Glimepiride in Adult Patients with Type 2 Diabetes Mellitusa
 | 24-Week Primary Time Point
 | Placebo | TRULICITY 1.5 mg
Intent-to-Treat (ITT) Population (N) | 60 | 239
HbA1c (%) (Mean)
Baseline | 8.4 | 8.4
Change from baselineb | -0.3 | -1.3
Difference from placebob (95% CI) |  | -1.1 (-1.4, -0.7)††
Percentage of patients HbA1c <7.0%c | 17 | 50††
Fasting Serum Glucose (mg/dL) (Mean)
Baseline | 175 | 178
Change from baselineb | 2 | -28
Difference from placebob (95% CI) |  | -30 (-44, -15)††
Body Weight (kg) (Mean)
Baseline | 89.5 | 84.5
Change from baselineb | -0.2 | -0.5
Difference from placebob (95% CI) |  | -0.4 (-1.2, 0.5)
Abbreviations: HbA1c = hemoglobin A1c.
a Intent-to-treat population. Data post-onset of rescue therapy are treated as missing. At Week 24 primary efficacy was missing for 10% and 12% of individuals randomized to TRULICITY 1.5 mg and placebo, respectively.
b Least-squares mean from ANCOVA adjusted for baseline value and other stratification factors. Placebo multiple imputation, with respect to the baseline values, was used to model a wash-out of the treatment effect for patients having missing Week 24 data.
c Patients with missing HbA1c data at Week 24 were considered as non-responders.
†† p<0.001 for superiority of TRULICITY 1.5 mg compared to placebo, overall type I error controlled.

Placebo- and Exenatide-Controlled Trial (Add-on to Metformin and Thiazolidinedione)

In this placebo-controlled trial with primary endpoint at 26 weeks, 976 adult patients were randomized to and received placebo, TRULICITY 0.75 mg once weekly, TRULICITY 1.5 mg once weekly, or exenatide 10 mcg BID, all as add-on to maximally tolerated doses of metformin (≥1500 mg per day) and pioglitazone (up to 45 mg per day). Exenatide treatment group assignment was open-label while the treatment assignments to placebo, TRULICITY 0.75 mg, and TRULICITY 1.5 mg were blinded. After 26 weeks, patients in the placebo treatment group were randomized to either TRULICITY 0.75 mg once weekly or TRULICITY 1.5 mg once weekly to maintain blinding. Randomization occurred after a 12-week lead-in period; during the initial 4 weeks of the lead-in period, patients were titrated to maximally tolerated doses of metformin and pioglitazone; this was followed by an 8-week glycemic stabilization period prior to randomization. Patients randomized to exenatide started at a dose of 5 mcg BID for 4 weeks and then were escalated to 10 mcg BID. Patients had a mean age of 56 years; mean duration of type 2 diabetes of 9 years; 58% were male; race: White, Black and Asian were 74%, 8% and 3%, respectively; and 81% of the trial population were in the US.

Treatment with TRULICITY 0.75 mg and 1.5 mg once weekly resulted in a statistically significant reduction in HbA1c compared to placebo (at 26 weeks) and compared to exenatide at 26 weeks (Table 8 and Figure 5). Over the 52-week trial period, the percentage of patients who required glycemic rescue was 8.9% in the TRULICITY 0.75 mg once weekly + metformin and pioglitazone treatment group, 3.2% in the TRULICITY 1.5 mg once weekly + metformin and pioglitazone treatment group, and 8.7% in the exenatide BID + metformin and pioglitazone treatment group.

Table 8: Results at Week 26 of TRULICITY Compared to Placebo and Exenatide, All as Add-On to Metformin and Thiazolidinedione in Adult Patients with Type 2 Diabetes Mellitusa
 | 26-Week Primary Time Point
 | Placebo | TRULICITY 0.75 mg | TRULICITY 1.5 mg | Exenatide 10 mcg BID
Intent-to-Treat (ITT) Population (N)‡ | 141 | 280 | 279 | 276
HbA1c (%) (Mean)
Baseline | 8.1 | 8.1 | 8.1 | 8.1
Change from baselineb | -0.5 | -1.3 | -1.5 | -1.0
Difference from placebob (95% CI) | - | -0.8 (-1.0, -0.7)‡‡ | -1.1 (-1.2, -0.9)‡‡ | -
Difference from exenatideb (95% CI) | - | -0.3 (-0.4, -0.2)†† | -0.5 (-0.7, -0.4)†† | -
Percentage of patients HbA1c <7.0% | 43 | 66**, ## | 78**, ## | 52
Fasting Serum Glucose (mg/dL) (Mean)
Baseline | 166 | 159 | 162 | 164
Change from baselineb | -5 | -34 | -42 | -24
Difference from placebob (95% CI) | - | -30 (-36, -23) | -38 (-45, -31) | -
Difference from exenatideb (95% CI) | - | -10 (-15, -5) | -18 (-24, -13) | -
Body Weight (kg) (Mean)
Baseline | 94.1 | 95.5 | 96.2 | 97.4
Change from baselineb | 1.2 | 0.2 | -1.3 | -1.1
Difference from placebob (95% CI) | - | -1.0 (-1.8, -0.3) | -2.5 (-3.3, -1.8) | -
Difference from exenatideb (95% CI) | - | 1.3 (0.6, 1.9) | -0.2 (-0.9, 0.4) | -
Abbreviations: BID = twice daily; HbA1c = hemoglobin A1c.
a Intent-to-treat population. Last observation carried forward (LOCF) was used to impute missing data. Data post-onset of rescue therapy are treated as missing. At Week 26, primary efficacy was missing for 23%, 10%, 7% and 12% of individuals randomized to placebo, TRULICITY 0.75 mg, TRULICITY 1.5 mg, and exenatide, respectively.
b Least-squares (LS) mean adjusted for baseline value and other stratification factors.
‡ Patients included in the analysis are a subset of the ITT population that had at least one post-baseline assessment. The primary analysis included 119, 269, 271 and 266 individuals randomized to placebo, TRULICITY 0.75 mg, TRULICITY 1.5 mg, and exenatide, respectively.
‡‡ Multiplicity adjusted 1-sided p-value <0.001, for superiority of TRULICITY compared to placebo, assessed only for HbA1c.
†† Multiplicity adjusted 1-sided p-value <0.001, for superiority of TRULICITY compared to exenatide, assessed only for HbA1c.
** p<0.001 TRULICITY compared to placebo, assessed only for HbA1c <7.0%.
## p<0.001 TRULICITY compared to exenatide, assessed only for HbA1c <7.0%.

Number of patients with observed data
Placebo | 141 |  | 108
TRULICITY 0.75 mg | 280 |  | 251
TRULICITY 1.5 mg | 279 |  | 259
Exenatide | 276 |  | 242
Mean HbA1c adjusted for baseline HbA1c and country.

Figure 5: Adjusted Mean HbA1c at Each Time Point (ITT, MMRM) and at Week 26 (ITT, LOCF)

Placebo-Controlled Trial (Add-on to SGLT2i, with or without Metformin)

In this 24-week placebo-controlled, double-blind trial, 423 adult patients were randomized to and received TRULICITY 0.75 mg, TRULICITY 1.5 mg, or placebo, as add-on to sodium-glucose co-transporter 2 inhibitor (SGLT2i) therapy (96% with and 4% without metformin). Trulicity was administered once weekly, and SGLT2i was administered according to the local country label. Patients had a mean age of 57 years; mean duration of type 2 diabetes of 9.4 years; 50% were male; race: White, Black, and Asian were 89%, 3%, and 0.2%, respectively; and 21% of the trial population was in the US.

At 24 weeks, treatment with once weekly TRULICITY 0.75 mg and 1.5 mg resulted in a statistically significant reduction from baseline in HbA1c compared to placebo (Table 9).

The mean baseline body weight was 90.5, 91.1, and 92.9 kg in the placebo, TRULICITY 0.75 mg, and TRULICITY 1.5 mg groups, respectively. The mean changes from baseline in body weight at Week 24 were -2.0, -2.5, and -2.9 kg for placebo, TRULICITY 0.75 mg, and TRULICITY 1.5 mg, respectively. The difference from placebo (95% CI) was -0.9 kg (-1.7, -0.1) for TRULICITY 1.5 mg.

Table 9: Results at Week 24 of TRULICITY as Add-on to SGLT2i in Adult Patients with Type 2 Diabetes Mellitusa
 | 24-Week Primary Time Point
 | Placebo | TRULICITY 0.75 mg | TRULICITY 1.5 mg
Intent-to-Treat (ITT) Population (N) | 140 | 141 | 142
HbA1c (%) (Mean)
Baseline | 8.1 | 8.1 | 8.0
Change from baselineb | -0.6 | -1.2 | -1.3
Difference from placebob (95% CI) | - | -0.7 (-0.8, -0.5)†† | -0.8 (-0.9, -0.6)††
Percentage of patients HbA1c <7.0%c | 31 | 59†† | 67††
Fasting Serum Glucose (mg/dL) (Mean)
Baseline | 153 | 162 | 161
Change from baselineb | -6 | -25 | -30
Difference from placebob (95% CI) | - | -19 (-25, -13) | -24 (-30, -18)††
Abbreviations: HbA1c = hemoglobin A1c; SGLT2i = sodium-glucose co-transporter-2 inhibitors.
a Intent-to-treat population. At Week 24, primary efficacy was missing for 3%, 4%, and 6% of individuals treated with placebo, TRULICITY 0.75 mg, and TRULICITY 1.5 mg, respectively.
b Least-squares mean adjusted for baseline value and other stratification factors. Placebo multiple imputation, using baseline and 24-week values from the placebo arm, was applied to model a washout of the treatment effect for patients missing 24-week values (HbA1c, fasting serum glucose, and body weight).
c Patients with missing HbA1c data at Week 24 were considered as non-responders.
†† p<0.001 for superiority of TRULICITY compared to placebo, overall type I error controlled.

Insulin Glargine Controlled Trial (Add-on to Metformin and Sulfonylurea)

In this open-label comparator trial (double-blind with respect to TRULICITY dose assignment) with primary endpoint at 52 weeks, 807 adult patients were randomized to and received TRULICITY 0.75 mg once weekly, TRULICITY 1.5 mg once weekly, or insulin glargine once daily, all as add-on to maximally tolerated doses of metformin and glimepiride. Randomization occurred after a 10-week lead-in period; during the initial 2 weeks of the lead-in period, patients were titrated to maximally tolerated doses of metformin and glimepiride. This was followed by a 6- to 8-week glycemic stabilization period prior to randomization.

Patients randomized to insulin glargine were started on a dose of 10 units once daily. Insulin glargine dose adjustments occurred twice weekly for the first 4 weeks of treatment based on self-measured fasting plasma glucose (FPG), followed by once weekly titration through Week 8 of treatment, utilizing an algorithm that targeted a fasting plasma glucose of <100 mg/dL. Only 24% of patients were titrated to goal at the 52-week primary endpoint. The dose of glimepiride could be reduced or discontinued after randomization (at the discretion of the investigator) in the event of persistent hypoglycemia. The dose of glimepiride was reduced or discontinued in 28%, 32%, and 29% of patients randomized to TRULICITY 0.75 mg, TRULICITY 1.5 mg, and glargine.

Patients had a mean age of 57 years; mean duration of type 2 diabetes of 9 years; 51% were male; race: White, Black and Asian were 71%, 1% and 17%, respectively; and 0% of the trial population were in the US.

Treatment with TRULICITY once weekly resulted in a reduction in HbA1c from baseline at 52 weeks when used in combination with metformin and sulfonylurea (Table 10). The difference in observed effect size between TRULICITY 0.75 mg and 1.5 mg, respectively, and glargine in this trial excluded the pre-specified non-inferiority margin of 0.4%.

Table 10: Results at Week 52 of TRULICITY Compared to Insulin Glargine, Both as Add-on to Metformin and Sulfonylurea in Adult Patients with Type 2 Diabetes Mellitusa
 | 52-Week Primary Time Point
 | TRULICITY 0.75 mg | TRULICITY 1.5 mg | Insulin Glargine
Intent-to-Treat (ITT) Population (N)‡ | 272 | 273 | 262
HbA1c (%) (Mean)
Baseline | 8.1 | 8.2 | 8.1
Change from baselineb | -0.8 | -1.1 | -0.6
Fasting Serum Glucose (mg/dL) (Mean)
Baseline | 161 | 165 | 163
Change from baselineb | -16 | -27 | -32
Difference from insulin glargineb (95% CI) | 16 (9, 23) | 5 (-2, 12) | -
Body Weight (kg) (Mean)
Baseline | 86.4 | 85.2 | 87.6
Change from baselineb | -1.3 | -1.9 | 1.4
Difference from insulinb (95% CI) | -2.8 (-3.4, -2.2) | -3.3 (-3.9, -2.7) | -
Abbreviations: HbA1c = hemoglobin A1c.
a Intent-to-treat population. Last observation carried forward (LOCF) was used to impute missing data. Data post-onset of rescue therapy are treated as missing. At Week 52, primary efficacy was missing for 17%, 13% and 12% of individuals randomized to TRULICITY 0.75 mg, TRULICITY 1.5 mg and glargine, respectively.
b Least-squares (LS) mean adjusted for baseline value and other stratification factors.
‡ Patients included in the analysis are a subset of the ITT population that had at least one post-baseline assessment. The primary analysis included 267, 263 and 259 individuals randomized to TRULICITY 0.75 mg, TRULICITY 1.5 mg, and glargine, respectively.

Placebo-Controlled Trial (Add-on to Basal Insulin, with or without Metformin)

In this 28-week placebo-controlled, double-blind trial, 300 adult patients were randomized to placebo or once weekly TRULICITY 1.5 mg, as add-on to titrated basal insulin glargine (with or without metformin). Patients had a mean age of 60 years; mean duration of type 2 diabetes of 13 years; 58% were male; race: White, Black, and Asian were 94%, 4%, and 0.3%, respectively; and 20% of the trial population was in the US.

The mean starting dose of insulin glargine was 37 units/day for patients receiving placebo and 41 units/day for patients receiving TRULICITY 1.5 mg. At randomization, the initial insulin glargine dose in patients with HbA1c <8.0% was reduced by 20%.

At 28 weeks, treatment with once weekly TRULICITY 1.5 mg resulted in a statistically significant reduction in HbA1c compared to placebo (Table 11).

Table 11: Results at Week 28 of TRULICITY Compared to Placebo as Add-On to Basal Insulin in Adult Patients with Type 2 Diabetes Mellitusa
 | 28-Week Primary Time Point
 | Placebo | TRULICITY 1.5 mg
Intent-to-Treat (ITT) Population (N) | 150 | 150
HbA1c (%) (Mean)
Baseline | 8.3 | 8.4
Change from baselineb | -0.7 | -1.4
Difference from placebob (95% CI) |  | -0.7 (-0.9, -0.5)††
Percentage of patients HbA1c <7.0% c | 33 | 67††
Fasting Serum Glucose (mg/dL) (Mean)
Baseline | 156 | 157
Change from baselineb | -30 | -44
Difference from placebob (95% CI) |  | -14 (-23, -4)†
Body Weight (kg) (Mean)
Baseline | 92.6 | 93.3
Change from baselineb | 0.8 | -1.3
Difference from placebob (95% CI) |  | -2.1 (-2.9, -1.4)††
Abbreviations: HbA1c = hemoglobin A1c.
a Intent-to-treat population. At Week 28, primary efficacy was missing for 12% and 8% of individuals randomized to placebo and TRULICITY 1.5 mg, respectively.
b Least-squares mean from ANCOVA adjusted for baseline value and other stratification factors. Placebo multiple imputation, with respect to baseline values, was used to model a wash-out of the treatment effect for patients having missing Week 28 data.
c Patients with missing HbA1c data at Week 28 were considered as non-responders.
†† p<0.001 for superiority of TRULICITY 1.5 mg compared to placebo, overall type I error controlled.
† p≤0.005 for superiority of TRULICITY 1.5 mg compared to placebo, overall type I error controlled.

Insulin Glargine-Controlled Trial (Combination with Prandial Insulin, with or without Metformin)

In this open-label comparator trial (double-blind with respect to TRULICITY dose assignment) with primary endpoint at 26 weeks, 884 adult patients on 1 or 2 insulin injections per day were enrolled. Randomization occurred after a 9-week lead-in period; during the initial 2 weeks of the lead-in period, patients continued their pre-trial insulin regimen but could be initiated and/or up-titrated on metformin, based on investigator discretion; this was followed by a 7-week glycemic stabilization period prior to randomization.

At randomization, patients discontinued their pre-trial insulin regimen and were randomized to TRULICITY 0.75 mg once weekly, TRULICITY 1.5 mg once weekly, or insulin glargine once daily, all in combination with prandial insulin lispro 3 times daily, with or without metformin. Insulin lispro was titrated in each arm based on preprandial and bedtime glucose, and insulin glargine was titrated to a fasting plasma glucose goal of <100 mg/dL. Only 36% of patients randomized to glargine were titrated to the fasting glucose goal at the 26-week primary timepoint.

Patients had a mean age of 59 years; mean duration of type 2 diabetes of 13 years; 54% were male; race: White, Black and Asian were 79%, 10% and 4%, respectively; and 33% of the trial population were in the US.

Treatment with TRULICITY 0.75 mg and 1.5 mg once weekly resulted in a reduction in HbA1c from baseline. The difference in observed effect size between TRULICITY 0.75 mg and 1.5 mg, respectively, and glargine in this trial excluded the pre-specified non-inferiority margin of 0.4% (Table 12).

Table 12: Results at Week 26 of TRULICITY Compared to Insulin Glargine, Both in Combination with Insulin Lispro in Adult Patients with Type 2 Diabetes Mellitusa
 | 26-Week Primary Time Point
 | TRULICITY 0.75 mg | TRULICITY 1.5 mg | Insulin Glargine
Intent-to-Treat (ITT) Population (N)‡ | 293 | 295 | 296
HbA1c (%) (Mean)
Baseline | 8.4 | 8.5 | 8.5
Change from baselineb | -1.6 | -1.6 | -1.4
Fasting Serum Glucose (mg/dL) (Mean)
Baseline | 150 | 157 | 154
Change from baselineb | 4 | -5 | -28
Difference from insulin glargineb (95% CI) | 32 (24, 41) | 24 (15, 32) | -
Body Weight (kg) (Mean)
Baseline | 91.7 | 91.0 | 90.8
Change from baselineb | 0.2 | -0.9 | 2.3
Difference from insulin glargineb (95% CI) | -2.2 (-2.8, -1.5) | -3.2 (-3.8, -2.6) | -
Abbreviation: HbA1c = hemoglobin A1c
a Intent-to-treat population. Last observation carried forward (LOCF) was used to impute missing data. Data post-onset of rescue therapy are treated as missing. At Week 26, primary efficacy was missing for 14%, 15%, and 14% of individuals randomized to TRULICITY 0.75 mg, TRULICITY 1.5 mg and glargine, respectively.
b Least-squares (LS) mean adjusted for baseline value and other stratification factors.
‡ Patients included in the analysis are a subset of the ITT population that had at least one post-baseline assessment. The primary analysis included 275, 273 and 276 individuals randomized to TRULICITY 0.75 mg, TRULICITY 1.5 mg, and glargine, respectively.

14.4 Glycemic Control Trials in Adults with Type 2 Diabetes Mellitus and Moderate to Severe Chronic Kidney Disease

In this open-label comparator trial (double-blind with respect to TRULICITY dose assignment) with primary endpoint at 26 weeks, a total of 576 adult patients with type 2 diabetes were randomized and treated to compare TRULICITY 0.75 mg and 1.5 mg with insulin glargine (NCT01621178).

Patients on insulin and other antidiabetic therapy (e.g., oral antidiabetic drugs, pramlintide) had non-insulin therapies discontinued and had their insulin dose adjusted for 12 weeks prior to randomization. Patients on insulin therapy alone maintained a stable insulin dose for 3 weeks prior to randomization. At randomization, patients discontinued their pre-trial insulin regimen and patients were randomized to TRULICITY 0.75 mg once weekly, TRULICITY 1.5 mg once weekly, or insulin glargine once daily, all in combination with prandial insulin lispro. For patients randomized to insulin glargine, the initial insulin glargine dose was based on the basal insulin dose prior to randomization. Insulin glargine was allowed to be titrated with a fasting plasma glucose goal of ≤150 mg/dL. Insulin lispro was allowed to be titrated with a preprandial and bedtime glucose goal of ≤180 mg/dL.

Patients had a mean age of 65 years; a mean duration of type 2 diabetes of 18 years; 52% were male; race: White, Black, and Asian were 69%, 16%, and 3%, respectively; and 32% of the trial population were in the US. At baseline, overall mean eGFR was 38 mL/min/1.73 m^2, 30% of patients had eGFR <30 mL/min/1.73 m^2, and 45% of patients had macroalbuminuria. Patients on over 70 units/day of basal insulin were excluded from the trial.

Treatment with TRULICITY 0.75 mg and 1.5 mg once weekly resulted in a reduction in HbA1c at 26-weeks from baseline. The difference in observed effect size between TRULICITY 0.75 mg and 1.5 mg, respectively, and glargine in this trial excluded the pre-specified non-inferiority margin of 0.4%. Mean fasting plasma glucose increased in the TRULICITY arms (Table 13).

Mean baseline body weight was 90.9 kg, 88.1 kg, and 88.2 kg in the TRULICITY 0.75 mg, TRULICITY 1.5 mg, and insulin glargine arms, respectively. The mean changes from baseline at Week 26 were -1.1, -2, and 1.9 kg in the TRULICITY 0.75 mg, TRULICITY 1.5 mg, and insulin glargine arms, respectively.

Table 13: Results at Week 26 of TRULICITY Compared to Insulin Glargine, Both in Combination with Insulin Lispro, in Patients with Moderate to Severe Chronic Kidney Disease in Adult Patients with Type 2 Diabetes Mellitusa
 | 26-Week Primary Time Point
 | TRULICITY 0.75 mg | TRULICITY 1.5 mg | Insulin Glargine
Intent-to-Treat Population (N) | 190 | 192 | 194
HbA1c (%) (Mean)
Baseline | 8.6 | 8.6 | 8.6
Change from baselineb | -0.9 | -1.0 | -1.0
Difference from insulin glargineb (95% CI) | 0.0 (-0.2, 0.3) | -0.1 (-0.3, 0.2)
Percentage of patients HbA1c <8.0% | 73 | 75 | 74
Fasting Serum Glucose (mg/dL) (Mean)
Baseline | 167 | 161 | 170
Change from baselineb | 6 | 14 | -23
Difference from insulin glargineb (95% CI) | 30 (16, 43) | 37 (24, 50)
Abbreviation: HbA1c = hemoglobin A1c
a Intent-to-treat population (all randomized and treated patients) was used in the analysis regardless of discontinuation of study drug or initiation of rescue therapy. At Week 26, primary efficacy was missing for 12%, 15%, and 9% of individuals randomized to and treated with TRULICITY 0.75 mg, TRULICITY 1.5 mg, and insulin glargine, respectively. Missing data were imputed using multiple imputation within treatment group.
b Least-squares (LS) mean from ANCOVA pattern mixture model adjusted for baseline value and other stratification factors.

14.5 Cardiovascular Outcomes Trial in Adults with Type 2 Diabetes Mellitus and Cardiovascular Disease or Multiple Cardiovascular Risk Factors

The REWIND trial (NCT01394952) was a multi-national, multi-center, randomized, placebo-controlled, double-blind trial. In this trial, 9901 adult patients with type 2 diabetes mellitus and established cardiovascular (CV) disease or multiple cardiovascular risk factors were randomized to TRULICITY 1.5 mg or placebo both added to standard of care. The median follow-up duration was 5.4 years. The primary endpoint was the time to the first occurrence of a composite 3-component Major Adverse Cardiovascular Events (MACE) outcome, which included CV death, non-fatal myocardial infarction (MI), and non-fatal stroke.

Patients eligible to enter the trial were 50 years of age or older who had type 2 diabetes mellitus, had an HbA1c value ≤9.5% with no lower limit at screening, and had either established CV disease, or did not have established CV disease but had multiple CV risk factors. Patients who were confirmed to have established CV disease (31.5% of randomized patients) had a history of at least one of the following: MI (16.2%); myocardial ischemia by a stress test or with cardiac imaging (9.3%); ischemic stroke (5.3%); coronary, carotid, or peripheral artery revascularization (18.0%); unstable angina (5.9%); or hospitalization for unstable angina with at least one of the following: ECG changes, myocardial ischemia on imaging, or a need for percutaneous coronary intervention (12.0%). Patients confirmed to be without established CV disease, but with multiple CV risk factors, comprised 62.8% of the randomized trial population.

At baseline, demographic and disease characteristics were balanced between treatment groups. Patients had a mean age of 66 years; 46% were female; race: White, Black, and Asian were 76%, 7%, and 4%, respectively.

The median baseline HbA1c was 7.2%. The mean duration of type 2 diabetes was 10.5 years and the mean BMI was 32.3 kg/m^2.

At baseline, 50.5% of patients had mild renal impairment (eGFR ≥60 but <90 mL/min/1.73m^2), 21.6% had moderate renal impairment (eGFR ≥30 but <60 mL/min/1.73m^2), and 1.1% of patients had severe renal impairment (eGFR <30 mL/min/1.73m^2) out of 9713 patients whose eGFR were available.

At baseline, 94.7% of patients were taking antidiabetic medication, with 10.5% of patients taking three or more antidiabetic drugs. The most common background antidiabetic drugs used at baseline were metformin (81.2%), sulfonylurea (46.0%), and insulin (23.9%). At baseline, CV disease and risk factors were managed with ACE inhibitors or angiotensin receptor blockers (81.5%), beta blockers (45.6%), calcium channel blockers (34.4%), diuretics (46.5%), statin therapy (66.1%), antithrombotic agents (58.7%), and aspirin (51.7%). During the trial, investigators were to modify anti-diabetic and cardiovascular medications to achieve local standard of care treatment targets with respect to blood glucose, lipids, and blood pressure, and manage patients recovering from an acute coronary syndrome or stroke event per local treatment guidelines.

For the primary analysis, a Cox proportional hazards model was used to test for superiority. Type I error was controlled across multiple tests. TRULICITY significantly reduced the risk of first occurrence of primary composite endpoint of CV death, non-fatal MI, or non-fatal stroke (HR: 0.88, 95% CI 0.79, 0.99). Refer to Figure 6 and Table 14.

Vital status was available for 99.7% of patients in the trial. A total of 1128 deaths were recorded during the REWIND trial. A majority of the deaths in the trial were adjudicated as CV deaths, and non-CV deaths were comparable between the treatment groups (4.4% in patients treated with TRULICITY and 5.0% in patients treated with placebo). There were 536 all-cause deaths (10.8%) in the dulaglutide group compared to 592 deaths (12.0%) in the placebo group.

Number of patients at risk
Placebo | 4952 | 4791 | 4625 | 4437 | 4275 | 3575 | 742
Dulaglutide | 4949 | 4815 | 4670 | 4521 | 4369 | 3686 | 741

Figure 6. KAPLAN MEIER CURVE: Time to First Occurrence of MACE in the REWIND Trial

Table 14: Treatment Effect for MACE and the Individual Components in the REWIND Trial, Median Trial Observation Time of 5.4 years in Adult Patients with Type 2 Diabetes Mellitusa
Time to First Occurrence of: | TRULICITY N=4949 | Placebo N=4952 | Hazard Ratio (95% CI) b
Composite of non-fatal myocardial infarction, non-fatal stroke, cardiovascular death (MACE)d | 594 (12.0%) | 663 (13.4%) | 0.88 (0.79, 0.99)c
Cardiovascular deathd,e | 317 (6.4%) | 346 (7.0%) | 0.91 (0.78, 1.06)
Non-fatal myocardial infarctiond,e | 205 (4.1%) | 212 (4.3%) | 0.96 (0.79, 1.16)
Non-fatal stroked,e | 135 (2.7%) | 175 (3.5%) | 0.76 (0.61, 0.95)
Fatal or non-fatal myocardial infarctiond,e | 223 (4.5%) | 231 (4.7%) | 0.96 (0.79, 1.15)
Fatal or non-fatal stroked,e | 158 (3.2%) | 205 (4.1%) | 0.76 (0.62, 0.94)
a All randomized patients.
b Cox-proportional hazards model with treatment as a factor. Type I error was controlled for the primary and secondary endpoints.
c p=0.026 for superiority (2-sided).
d Number and percentage of patients with events.
e Results for components of MACE, fatal and non-fatal stroke, and fatal and non-fatal MI are listed descriptively for supportive purposes. No statistical significance should be inferred since these CIs are not adjusted for multiplicity.

14.6 Glycemic Control Trial in Pediatric Patients 10 Years of Age and Older with Type 2 Diabetes Mellitus

In this 26-week randomized, double-blind, placebo-controlled, parallel-arm, multicenter trial with an open-label extension for an additional 26 weeks,154 pediatric patients 10 years of age and older with type 2 diabetes mellitus, who had inadequate glycemic control despite diet and exercise, were randomized to subcutaneous TRULICITY once weekly (0.75 mg and 1.5 mg) or subcutaneous placebo once weekly in combination with or without metformin and/or basal insulin treatment (NCT02963766).

Overall, in this trial demographic and baseline disease characteristics were comparable across the treatment groups. At baseline, 71% of patients were female, and the mean age was 14.5 years (ranging from 10 to 17 years). Overall, 55% were White, 15% were Black or African American, 12% were Asian, 10% were American Indian or Alaska Native, 5% were other races, and 3% had unknown race. Additionally, 55% were Hispanic or Latino, 42% were not Hispanic or Latino, and 3% had unknown ethnicity. At baseline, the mean duration of type 2 diabetes mellitus was 2 years, mean HbA1c was 8.1%, mean weight was 90.5 kg and mean BMI was 34.1 kg/m^2.

In this trial, once weekly TRULICITY (0.75 mg and 1.5 mg, pooled) (with or without metformin and/or basal insulin) was superior to placebo (p<0.001) in the change from baseline at Week 26 in HbA1c in pediatric patients 10 years of age and older with type 2 diabetes mellitus (see Table 15).

Table 15: Glycemic Results at Week 26 in Pediatric Patients 10 Years of Age and Older with Type 2 Diabetes Mellitus with Inadequate Glycemic Control Despite Diet and Exercise (With or Without Metformin and/or Basal Insulin)
 | Placebo | TRULICITY 0.75 mg once weekly | TRULICITY 1.5 mg once weekly | TRULICITY once weekly Pooleda
Intent-to-Treat Population (N) | 51 | 51 | 52 | 103
HbA1c (%) (Mean) c
Baseline Change from baseline at Week 26b Difference from placebo (95% CI)b | 8.1 0.6 - | 7.9 -0.6 -1.2 (-1.8, -0.6) | 8.2 -0.9 -1.5 (-2.1, -0.9) | 8.0 -0.8 -1.4 (-1.9, -0.8)
Percentage of Patients with HbA1c <7.0% at Week 26 d | 14% | 55% | 48% | 52%
Fasting Blood Glucose (mg/dL) (Mean) c
Baseline Change from baseline at Week 26b Difference from placebo (95% CI)b | 159 17.1 - | 149 -12.8 -29.9 (-50.7, -9.1) | 163 -24.9 -42.0 (-63.0, -20.9) | 156 -18.9 -35.9 (-54.2, -17.6)
Abbreviations: HbA1c = hemoglobin A1c.
a Combined results for TRULICITY 0.75 mg and 1.5 mg. The comparison of the two dosages together and individually with placebo was prespecified with overall type I error controlled.
b The change from baseline and difference from placebo were analyzed using analysis of covariance with effects for treatment, the baseline value as a covariate, and stratification factors which were HbA1c at screening (< 8% vs >= 8%), insulin use at baseline (yes/no), metformin use at baseline (yes/no).
c For HbA1c and Fasting Blood Glucose, multiple imputation was performed for missing data guided by washout method. At Week 26 primary efficacy (HbA1c) was missing for 8%, 6%, and 10% of patients on placebo, TRULICITY 0.75 mg and TRULICITY 1.5 mg respectively.
d For percentage of patients HbA1c < 7%, missing data was imputed as not achieving the target.

16 HOW SUPPLIED/STORAGE AND HANDLING

16.1 How Supplied

TRULICITY (dulaglutide) injection is a clear and colorless solution supplied in single-dose pens. TRULICITY is packaged in a cardboard outer carton containing 4 single-dose TRULICITY pens and is supplied as follows:

Total Strength per Total Volume | NDC
0.75 mg/0.5 mL | NDC 0002-1433-80
1.5 mg/0.5 mL | NDC 0002-1434-80
3 mg/0.5 mL | NDC 0002-2236-80
4.5 mg/0.5 mL | NDC 0002-3182-80

16.2 Storage and Handling

- Store TRULICITY in the refrigerator at 36°F to 46°F (2°C to 8°C).
- If needed, each single-dose pen can be kept at room temperature, not to exceed 86°F (30°C) for a total of 14 days.
- Do not freeze TRULICITY. Do not use TRULICITY if it has been frozen.
- Protect TRULICITY from light. Storage of TRULICITY in the original carton is recommended until time of administration.

17 PATIENT COUNSELING INFORMATION

Advise the patient to read the FDA-approved patient labeling (Medication Guide and Instructions for Use).

- Risk of Thyroid C-cell Tumors
  Inform patients that TRULICITY causes benign and malignant thyroid C-cell tumors in rats and that the human relevance of this finding has not been determined. Counsel patients to report symptoms of thyroid tumors (e.g., a lump in the neck, persistent hoarseness, dysphagia, or dyspnea) to their physician [see Boxed Warning and Warnings and Precautions (5.1)].
- Acute Pancreatitis
  Inform patients of the potential risk for acute pancreatitis and its symptoms: severe abdominal pain that may radiate to the back, and which may or may not be accompanied by vomiting. Instruct patients to discontinue TRULICITY promptly and contact their physician if pancreatitis is suspected [see Warnings and Precautions (5.2)].
- Hypoglycemia with Concomitant Use of Insulin Secretagogues or Insulin
  Inform patients that the risk of hypoglycemia may be increased when TRULICITY is used in combination with an insulin secretagogue (such as a sulfonylurea) or insulin. Educate patients on the signs and symptoms of hypoglycemia [see Warnings and Precautions (5.3)].
- Hypersensitivity Reactions
  Inform patients that serious hypersensitivity reactions have been reported during postmarketing use of TRULICITY. Advise patients on the symptoms of hypersensitivity reactions and instruct them to stop taking TRULICITY and seek medical advice promptly if such symptoms occur [see Warnings and Precautions (5.4)].
- Acute Kidney Injury Due to Volume Depletion
  Inform patients of the potential risk of acute kidney injury due to dehydration associated with gastrointestinal adverse reactions. Advise patients to take precautions to avoid fluid depletion. Inform patients of the signs and symptoms of acute kidney injury and instruct them to promptly report any of these signs or symptoms or persistent (or extended) nausea, vomiting, and diarrhea to their healthcare provider [see Warnings and Precautions (5.5)].
- Severe Gastrointestinal Adverse Reactions
  Inform patients of the potential risk of severe gastrointestinal adverse reactions. Instruct patients to contact their healthcare provider if they have severe or persistent gastrointestinal symptoms [see Warnings and Precautions (5.6)].
- Diabetic Retinopathy Complications in Patients with a History of Diabetic Retinopathy
  Inform patients to contact their physician if changes in vision are experienced during treatment with TRULICITY [see Warnings and Precautions (5.7)].
- Acute Gallbladder Disease
  Inform patients of the potential risk for cholelithiasis or cholecystitis. Instruct patients to contact their physician if cholelithiasis or cholecystitis is suspected for appropriate clinical follow-up [see Warnings and Precautions (5.8)].
- Pulmonary Aspiration During General Anesthesia or Deep Sedation
  Inform patients that TRULICITY may cause their stomach to empty more slowly which may lead to complications with anesthesia or deep sedation during planned surgeries or procedures. Instruct patients to inform healthcare providers prior to any planned surgeries or procedures if they are taking TRULICITY [see Warnings and Precautions (5.9)].
- Pregnancy
  Advise patients to inform their healthcare provider if they are pregnant or intend to become pregnant [see Use in Specific Populations (8.1)].
- Missed Dose
  Inform patients if a dose is missed and there are at least 3 days (72 hours) until the next scheduled dose, they should administer it as soon as possible and then resume their usual once weekly dosing schedule. If a dose is missed and the next regularly scheduled dose is due in 1 or 2 days, inform the patient to not administer the missed dose and instead resume TRULICITY with the next regularly scheduled dose [see Dosage and Administration (2.3)].

Eli Lilly and Company, Indianapolis, IN 46285, USA

US License Number 1891

Copyright © 2014, 2025, Eli Lilly and Company. All rights reserved.

Pat.: www.lilly.com/patents

TRU-0020-USPI-20250613

Medication Guide
TRULICITY® (TRU-li-si-tee)
(dulaglutide)
injection, for subcutaneous use

Read this Medication Guide before you start using TRULICITY and each time you get a refill. There may be new information. This information does not take the place of talking to your healthcare provider about your medical condition or your treatment.

What is the most important information I should know about TRULICITY?
TRULICITY may cause serious side effects, including:

- Possible thyroid tumors, including cancer. Tell your healthcare provider if you get a lump or swelling in your neck, hoarseness, trouble swallowing, or shortness of breath. These may be symptoms of thyroid cancer. In studies with rats or mice, TRULICITY and medicines that work like TRULICITY caused thyroid tumors, including thyroid cancer. It is not known if TRULICITY will cause thyroid tumors or a type of thyroid cancer called medullary thyroid carcinoma (MTC) in people.
- Do not use TRULICITY if you or any of your family have ever had a type of thyroid cancer called medullary thyroid carcinoma (MTC), or if you have an endocrine system condition called Multiple Endocrine Neoplasia syndrome type 2 (MEN 2).

What is TRULICITY?

- TRULICITY is an injectable prescription medicine that is used:
  - along with diet and exercise to improve blood sugar (glucose) in adults and children 10 years of age and older with type 2 diabetes mellitus.
  - to reduce the risk of major cardiovascular events such as death, heart attack, or stroke in adults with type 2 diabetes mellitus with known heart disease or multiple cardiovascular risk factors.
- It is not known if TRULICITY is safe and effective to lower blood sugar (glucose) in children under 10 years of age.

Do not use TRULICITY if:

- you or any of your family have ever had a type of thyroid cancer called MTC or if you have an endocrine system condition called MEN 2.
- you have had a serious allergic reaction to dulaglutide or any of the ingredients in TRULICITY. See the end of this Medication Guide for a complete list of ingredients in TRULICITY. See "What are the possible side effects of TRULICITY?" for symptoms of a serious allergic reaction.

Before using TRULICITY, tell your healthcare provider about all of your medical conditions, including if you:

- have or have had problems with your pancreas.
- have severe problems with your stomach, such as slowed emptying of your stomach (gastroparesis) or problems with digesting food.
- have a history of diabetic retinopathy.
- are scheduled to have surgery or other procedures that use anesthesia or deep sleepiness (deep sedation).
- are pregnant or plan to become pregnant. It is not known if TRULICITY will harm your unborn baby. Tell your healthcare provider if you become pregnant while using TRULICITY.
- are breastfeeding or plan to breastfeed. It is not known if TRULICITY passes into your breast milk. You and your healthcare provider should decide if you should breastfeed while taking TRULICITY.

Tell your healthcare provider about all the medicines you take, including prescription and over-the-counter medicines, vitamins, and herbal supplements. TRULICITY may affect the way some medicines work, and some medicines may affect the way TRULICITY works.
Before using TRULICITY, talk to your healthcare provider about low blood sugar and how to manage it. Tell your healthcare provider if you are taking other medicines to treat diabetes, including insulin or sulfonylureas.
Know the medicines you take. Keep a list of them to show your healthcare provider and pharmacist when you get a new medicine.

How should I use TRULICITY?

- Read the Instructions for Use that comes with TRULICITY.
- Use TRULICITY exactly as your healthcare provider tells you to.
- Your healthcare provider should show you how to use TRULICITY before you use it for the first time.
- Inject TRULICITY under the skin (subcutaneously) of your stomach (abdomen), thigh, or upper arm. Do not inject TRULICITY into a muscle (intramuscularly) or vein (intravenously).
- Use TRULICITY 1 time each week on the same day each week at any time of the day.
- You may change the day of the week as long as your last dose was given 3 or more days before.
- If you miss a dose of TRULICITY, take the missed dose as soon as possible if there are at least 3 days (72 hours) until your next scheduled dose. If there are less than 3 days remaining, skip the missed dose and take your next dose on the regularly scheduled day. Do not take 2 doses of TRULICITY within 3 days of each other.
- TRULICITY may be taken with or without food.
- Do not mix insulin and TRULICITY together in the same injection.
- You may give an injection of TRULICITY and insulin in the same body area (such as, your stomach area), but not right next to each other.
- Change (rotate) your injection site with each weekly injection. Do not use the same site for each injection.
- If you take too much TRULICITY, call your healthcare provider or Poison Helpline at 1-800-222-1222 or go to the nearest hospital emergency room right away.

What are the possible side effects of TRULICITY?
TRULICITY may cause serious side effects, including:

- See “What is the most important information I should know about TRULICITY?”
- inflammation of your pancreas (pancreatitis). Stop using TRULICITY and call your healthcare provider right away if you have severe pain in your stomach area (abdomen) that will not go away, with or without vomiting. You may feel the pain from your abdomen to your back.
- low blood sugar (hypoglycemia). Your risk for getting low blood sugar may be higher if you use TRULICITY with another medicine that can cause low blood sugar, such as a sulfonylurea or insulin.
  Signs and symptoms of low blood sugar may include:
  - dizziness or light-headedness
  - sweating
  - confusion or drowsiness
  - headache
  - blurred vision
  - slurred speech
  - shakiness
  - fast heartbeat
  - anxiety, irritability, or mood changes
  - hunger
  - weakness
  - feeling jittery
- serious allergic reactions. Stop using TRULICITY and get medical help right away if you have any symptoms of a serious allergic reaction including:
  - swelling of your face, lips, tongue or throat
  - problems breathing or swallowing
  - severe rash or itching
  - fainting or feeling dizzy
  - very rapid heartbeat
- dehydration leading to kidney problems. Diarrhea, nausea, and vomiting may cause a loss of fluids (dehydration) which may cause kidney problems. It is important for you to drink fluids to help reduce your chance of dehydration. Tell your healthcare provider right away if you have nausea, vomiting, or diarrhea that does not go away.
- severe stomach problems. Stomach problems, sometimes severe, have been reported in people who use TRULICITY. Tell your healthcare provider if you have stomach problems that are severe or will not go away.
- changes in vision. Tell your healthcare provider if you have changes in vision during treatment with TRULICITY.
- gallbladder problems. Gallbladder problems have happened in some people who take TRULICITY. Tell your healthcare provider right away if you get symptoms of gallbladder problems, which may include:
  - pain in your upper stomach (abdomen)
  - fever
  - yellowing of skin or eyes (jaundice)
  - clay-colored stools
- food or liquid getting into the lungs during surgery or other procedures that use anesthesia or deep sleepiness (deep sedation). TRULICITY may increase the chance of food getting into your lungs during surgery or other procedures. Tell all your healthcare providers that you are taking TRULICITY before you are scheduled to have surgery or other procedures.

The most common side effects of TRULICITY may include:

- nausea
- diarrhea
- vomiting

- stomach (abdominal) pain
- decreased appetite

Tell your healthcare provider if you have any side effect that bothers you or that does not go away. These are not all the possible side effects of TRULICITY. Call your doctor for medical advice about side effects. You may report side effects to FDA at 1-800-FDA-1088.

General information about the safe and effective use of TRULICITY.
Medicines are sometimes prescribed for purposes other than those listed in a Medication Guide. Do not use TRULICITY for a condition for which it was not prescribed. Do not give TRULICITY to other people, even if they have the same symptoms you have. It may harm them.
This Medication Guide summarizes the most important information about TRULICITY. If you would like more information, talk with your healthcare provider. You can ask your pharmacist or healthcare provider for information about TRULICITY that is written for health professionals.

What are the ingredients in TRULICITY?
Active ingredient: dulaglutide
Inactive ingredients: citric acid anhydrous, mannitol, polysorbate 80, trisodium citrate dihydrate, in water for injection
TRULICITY® is a registered trademark of Eli Lilly and Company.
Manufactured by: Eli Lilly and Company, Indianapolis, IN 46285, USA, US License Number 1891
www.TRULICITY.com.
Copyright © 2014, 2025, Eli Lilly and Company. All rights reserved.
For more information, go to www.TRULICITY.com or call 1-800-545-5979.

This Medication Guide has been approved by the U.S. Food and Drug Administration

Revised: May 2025

TRU-0011-MG-20250528

TRULICITY 0.75 MG SINGLE-DOSE PEN INSTRUCTIONS FOR USE

Instructions for Use

TRULICITY® (TRU-li-si-tee)
(dulaglutide)
injection, for subcutaneous use
0.75 mg/0.5 mL Single-Dose Pen
use 1 time each week (once weekly)

Information About TRULICITY Single-Dose Pen
Please read this Instructions for Use and the Medication Guide carefully and completely before using your TRULICITY Single-Dose Pen. Talk to your healthcare provider about how to inject TRULICITY the right way.

- TRULICITY Single-Dose Pen (Pen) is a disposable, prefilled medicine delivery device. Each Pen contains 1 dose of TRULICITY (0.75 mg/0.5 mL). Each Pen should only be used 1 time.
- TRULICITY is used 1 time each week.

You may want to mark your calendar to remind you when to take your next dose.

Before You Get Started
Remove | Check | Inspect | Prepare
Remove the Pen from the refrigerator. Leave the Base Cap on until you are ready to inject. | Check the Pen label to make sure you have the right medicine and it has not expired. | Check the Pen to make sure that it is not damaged and inspect the medicine to make sure it is not cloudy, discolored or has particles in it. | Wash your hands.
Choose Your Injection Site
Your healthcare provider can help you choose the injection site that is best for you.

Change (rotate) your injection site each week. You may use the same area of your body, but be sure to choose a different injection site in that area.
You may inject the medicine into your stomach (abdomen) or thigh.

Another person should give you the injection in the back of your upper arm.

Step 1 Uncap the Pen; Make sure the Pen is locked.; - Pull the Base Cap straight off and throw it away in your household trash. Do not put the Base Cap back on — this could damage the needle. Do not touch the needle.
Step 2 Place and Unlock; - Place the Clear Base flat and firmly against your skin at the injection site. Unlock by turning the Lock Ring.
Step 3 Press and Hold; - Press and hold the green Injection Button. You will hear a loud click. Continue holding the Clear Base firmly against your skin until you hear a second click. This happens when the needle starts retracting in about 5-10 seconds. - Remove the Pen from your skin. | You will know your injection is complete when the gray plunger is visible.

Important Information
Disposal of Pen
Storage and Handling
Commonly Asked Questions
Other Information
Where to Learn More

Disposing of Your Used Pens

- Put your used Pens in a FDA-cleared sharps disposal container right away after use. Do not throw away (dispose of) Pens in your household trash.
- If you do not have a FDA-cleared sharps disposal container, you may use a household container that is:
  - made of a heavy-duty plastic,
  - can be closed with a tight-fitting, puncture-resistant lid, without sharps being able to come out,
  - upright and stable during use,
  - leak-resistant, and
  - properly labeled to warn of hazardous waste inside the container.
- When your sharps disposal container is almost full, you will need to follow your community guidelines for the right way to dispose of your sharps disposal container. There may be state or local laws about how you should throw away used needles and syringes. For more information about safe sharps disposal, and for specific information about sharps disposal in the state that you live in, go to the FDA's website at: http://www.fda.gov/safesharpsdisposal.
- Do not recycle your used sharps disposal container.

Storage and Handling

- Store your Pen in the refrigerator between 36°F to 46°F (2°C to 8°C).
- You may store your Pen at room temperature below 86°F (30°C) for up to a total of 14 days.
- Do not freeze your Pen. If the Pen has been frozen, throw the Pen away and use a new Pen.
- Storage of your Pen in the original carton is recommended. Protect your Pen from direct heat and light.
- The Pen has glass parts. Handle it carefully. If you drop it on a hard surface, do not use it. Use a new Pen for your injection.
- Keep your TRULICITY Pen and all medicines out of the reach of children.

Commonly Asked Questions

What if I see air bubbles in my Pen?
Air bubbles are normal.
What if I unlock the Pen and press the green Injection Button before pulling off the Base Cap?
Do not remove the Base Cap. Throw away the Pen and get a new Pen.
What if there is a drop of liquid on the tip of the needle when I remove the Base Cap?
A drop of liquid on the tip of the needle is normal.
Do I need to hold the Injection Button down until the injection is complete?
This is not necessary, but it may help you keep the Pen steady and firm against your skin.
I heard more than 2 clicks during my injection—2 louder clicks and 1 soft one. Did I get my complete injection?
Some patients may hear a soft click right before the second loud click. That is the normal operation of the Pen. Do not remove the Pen from your skin until you hear the second louder click.
What if there is a drop of liquid or blood on my skin after my injection?
This is normal.
I am not sure if my Pen worked the right way.
Check to see if you have received your dose. Your dose was delivered the right way if the gray plunger is visible (see step 3). Also contact Lilly at 1-800-Lilly-Rx (1-800-545-5979) for further instructions. Until then, store your Pen safely to avoid an accidental needle stick.

Other Information

- If you have vision problems, do not use your Pen without help from a person trained to use the TRULICITY Pen.

Where to Learn More

- If you have any questions or problems with your TRULICITY Single-Dose Pen, contact Lilly at 1-800-Lilly-Rx (1-800-545-5979) or call your healthcare provider.
- For more information about TRULICITY Single-Dose Pen, visit our website at: www.trulicity.com.

SCAN THIS CODE TO LAUNCH
www.trulicity.com

This Instructions for Use has been approved by the U.S. Food and Drug Administration.
Eli Lilly and Company
Indianapolis, IN 46285, USA
US License Number 1891
TRULICITY is a registered trademark of Eli Lilly and Company.
Copyright © 2014, 2022, Eli Lilly and Company. All rights reserved.
The TRULICITY Pen meets the current dose accuracy and functional requirements of ISO 11608-1:2012 and 11608-5:2012.
Revised: 11/2022
TRULOAI-0004-IFU-20221117

TRULICITY 1.5 MG SINGLE-DOSE PEN INSTRUCTIONS FOR USE

Instructions for Use

TRULICITY® (TRU-li-si-tee)
(dulaglutide)
injection, for subcutaneous use
1.5 mg/0.5 mL Single-Dose Pen
use 1 time each week (once weekly)

Information About TRULICITY Single-Dose Pen
Please read this Instructions for Use and the Medication Guide carefully and completely before using your TRULICITY Single-Dose Pen. Talk to your healthcare provider about how to inject TRULICITY the right way.

- TRULICITY Single-Dose Pen (Pen) is a disposable, prefilled medicine delivery device. Each Pen contains 1 dose of TRULICITY (1.5 mg/0.5 mL). Each Pen should only be used 1 time.
- TRULICITY is used 1 time each week.

You may want to mark your calendar to remind you when to take your next dose.

Before You Get Started
Remove | Check |  | Inspect | Prepare
Remove the Pen from the refrigerator. Leave the Base Cap on until you are ready to inject. | Check the Pen label to make sure you have the right medicine and it has not expired. |  | Check the Pen to make sure that it is not damaged and inspect the medicine to make sure it is not cloudy, discolored or has particles in it. | Wash your hands.
Choose Your Injection Site
Your healthcare provider can help you choose the injection site that is best for you.

Change (rotate) your injection site each week. You may use the same area of your body, but be sure to choose a different injection site in that area.
You may inject the medicine into your stomach (abdomen) or thigh.

Another person should give you the injection in the back of your upper arm.

Step 1 Uncap the Pen; Make sure the Pen is locked.; - Pull the Base Cap straight off and throw it away in your household trash. Do not put the Base Cap back on — this could damage the needle. Do not touch the needle.
Step 2 Place and Unlock; - Place the Clear Base flat and firmly against your skin at the injection site. Unlock by turning the Lock Ring.
Step 3 Press and Hold; - Press and hold the green Injection Button. You will hear a loud click. Continue holding the Clear Base firmly against your skin until you hear a second click. This happens when the needle starts retracting in about 5-10 seconds. - Remove the Pen from your skin. | You will know your injection is complete when the gray plunger is visible.

Important Information
Disposal of Pen
Storage and Handling
Commonly Asked Questions
Other Information
Where to Learn More

Disposing of Your Used Pens

- Put your used Pens in a FDA-cleared sharps disposal container right away after use. Do not throw away (dispose of) Pens in your household trash.
- If you do not have a FDA-cleared sharps disposal container, you may use a household container that is:
  - made of a heavy-duty plastic,
  - can be closed with a tight-fitting, puncture-resistant lid, without sharps being able to come out,
  - upright and stable during use,
  - leak-resistant, and
  - properly labeled to warn of hazardous waste inside the container.
- When your sharps disposal container is almost full, you will need to follow your community guidelines for the right way to dispose of your sharps disposal container. There may be state or local laws about how you should throw away used needles and syringes. For more information about safe sharps disposal, and for specific information about sharps disposal in the state that you live in, go to the FDA's website at: http://www.fda.gov/safesharpsdisposal.
- Do not recycle your used sharps disposal container.

Storage and Handling

- Store your Pen in the refrigerator between 36°F to 46°F (2°C to 8°C).
- You may store your Pen at room temperature below 86°F (30°C) for up to a total of 14 days.
- Do not freeze your Pen. If the Pen has been frozen, throw the Pen away and use a new Pen.
- Storage of your Pen in the original carton is recommended. Protect your Pen from direct heat and light.
- The Pen has glass parts. Handle it carefully. If you drop it on a hard surface, do not use it. Use a new Pen for your injection.
- Keep your TRULICITY Pen and all medicines out of the reach of children.

Commonly Asked Questions

What if I see air bubbles in my Pen?
Air bubbles are normal.
What if I unlock the Pen and press the green Injection Button before pulling off the Base Cap?
Do not remove the Base Cap. Throw away the Pen and get a new Pen.
What if there is a drop of liquid on the tip of the needle when I remove the Base Cap?
A drop of liquid on the tip of the needle is normal.
Do I need to hold the Injection Button down until the injection is complete?
This is not necessary, but it may help you keep the Pen steady and firm against your skin.
I heard more than 2 clicks during my injection—2 louder clicks and 1 soft one. Did I get my complete injection?
Some patients may hear a soft click right before the second loud click. That is the normal operation of the Pen. Do not remove the Pen from your skin until you hear the second louder click.
What if there is a drop of liquid or blood on my skin after my injection?
This is normal.
I am not sure if my Pen worked the right way.
Check to see if you have received your dose. Your dose was delivered the right way if the gray plunger is visible (see step 3). Also contact Lilly at 1-800-Lilly-Rx (1-800-545-5979) for further instructions. Until then, store your Pen safely to avoid an accidental needle stick.

Other Information

- If you have vision problems, do not use your Pen without help from a person trained to use the TRULICITY Pen.

Where to Learn More

- If you have any questions or problems with your TRULICITY Single-Dose Pen, contact Lilly at 1-800-Lilly-Rx (1-800-545-5979) or call your healthcare provider.
- For more information about TRULICITY Single-Dose Pen, visit our website at: www.trulicity.com.

SCAN THIS CODE TO LAUNCH
www.trulicity.com

This Instructions for Use has been approved by the U.S. Food and Drug Administration.
Eli Lilly and Company
Indianapolis, IN 46285, USA
US License Number 1891
TRULICITY is a registered trademark of Eli Lilly and Company.
Copyright © 2014, 2022, Eli Lilly and Company. All rights reserved.
The TRULICITY Pen meets the current dose accuracy and functional requirements of ISO 11608-1:2012 and 11608-5:2012.
Revised: 11/2022
TRUHIAI-0004-IFU-20221117

TRULICITY 3 MG SINGLE-DOSE PEN INSTRUCTIONS FOR USE

Instructions for Use

TRULICITY® (TRU-li-si-tee)
(dulaglutide)
injection, for subcutaneous use
3 mg/0.5 mL Single-Dose Pen
use 1 time each week (once weekly)

Information About TRULICITY Single-Dose Pen

Please read this Instructions for Use and the Medication Guide carefully and completely before using your TRULICITY Single-Dose Pen. Talk to your healthcare provider about how to inject TRULICITY the right way.

- TRULICITY Single-Dose Pen (Pen) is a disposable, prefilled medicine delivery device. Each Pen contains 1 dose of TRULICITY (3 mg/0.5 mL). Each Pen should only be used 1 time.
- TRULICITY is used 1 time each week. You may want to mark your calendar to remind you when to take your next dose.

Before You Get Started

Remove

Check

Inspect

Prepare

Remove the Pen from the refrigerator.
Leave the Base Cap on until you are ready to inject.

Check the Pen label to make sure you have the right medicine and it has not expired.
Expiration Date

Check the Pen to make sure that it is not damaged and inspect the medicine to make sure it is not cloudy, discolored or has particles in it.

Wash your hands.

Choose Your Injection Site

Your healthcare provider can help you choose the injection site that is best for you.

Change (rotate) your injection site each week. You may use the same area of your body, but be sure to choose a different injection site in that area.
You may inject the medicine into your stomach (abdomen) or thigh.

Another person should give you the injection in the back of your upper arm.

Step 1 Uncap the Pen
Make sure the Pen is locked.

- Pull the Base Cap straight off and throw it away in your household trash.
  Do not put the Base Cap back on — this could damage the needle.
  Do not touch the needle.

Step 2 Place and Unlock

- Place the Clear Base flat and firmly against your skin at the injection site.

Unlock by turning the Lock Ring.

Step 3 Press and Hold

- Press and hold the green Injection Button. You will hear a loud click.
  Continue holding the Clear Base firmly against your skin until you hear a second click. This happens when the needle starts retracting in about 5-10 seconds.
- Remove the Pen from your skin.

Important Information

Disposal of Pen

Storage and Handling

Commonly Asked Questions

Other Information

Where to Learn More

Disposing of Your Used Pens

- Put your used Pens in a FDA-cleared sharps disposal container right away after use. Do not throw away (dispose of) Pens in your household trash.
- If you do not have a FDA-cleared sharps disposal container, you may use a household container that is:
  - made of a heavy-duty plastic,
  - can be closed with a tight-fitting, puncture-resistant lid, without sharps being able to come out,
  - upright and stable during use,
  - leak-resistant, and
  - properly labeled to warn of hazardous waste inside the container.
- When your sharps disposal container is almost full, you will need to follow your community guidelines for the right way to dispose of your sharps disposal container. There may be state or local laws about how you should throw away used needles and syringes. For more information about safe sharps disposal, and for specific information about sharps disposal in the state that you live in, go to the FDA's website at: http://www.fda.gov/safesharpsdisposal.
- Do not recycle your used sharps disposal container.

Storage and Handling

- Store your Pen in the refrigerator between 36°F to 46°F (2°C to 8°C).
- You may store your Pen at room temperature below 86°F (30°C) for a total of 14 days.
- Do not freeze your Pen. If the Pen has been frozen, throw the Pen away and use a new Pen.
- Storage of your Pen in the original carton is recommended. Protect your Pen from direct heat and light.
- The Pen has glass parts. Handle it carefully. If you drop it on a hard surface, do not use it. Use a new Pen for your injection.
- Keep your TRULICITY Pen and all medicines out of the reach of children.

Commonly Asked Questions

What if I see air bubbles in my Pen?

Air bubbles are normal.

What if I unlock the Pen and press the green Injection Button before pulling off the Base Cap?

Do not remove the Base Cap. Throw away the Pen and get a new Pen.

What if there is a drop of liquid on the tip of the needle when I remove the Base Cap?

A drop of liquid on the tip of the needle is normal.

Do I need to hold the Injection Button down until the injection is complete?

This is not necessary, but it may help you keep the Pen steady and firm against your skin.

I heard more than 2 clicks during my injection—2 louder clicks and 1 soft one. Did I get my complete injection?

Some people may hear a soft click right before the second loud click. That is the normal operation of the Pen. Do not remove the Pen from your skin until you hear the second louder click.

What if there is a drop of liquid or blood on my skin after my injection?

This is normal.

I am not sure if my Pen worked the right way.

Check to see if you have received your dose. Your dose was delivered the right way if the gray plunger is visible (see step 3). Also contact Lilly at 1-800-Lilly-Rx (1-800-545-5979) for further instructions. Until then, store your Pen safely to avoid an accidental needle stick.

Other Information

- If you have vision problems, do not use your Pen without help from a person trained to use the TRULICITY Pen.

Where to Learn More

- If you have any questions or problems with your TRULICITY Single-Dose Pen, contact Lilly at 1-800-Lilly-Rx (1-800-545-5979) or call your healthcare provider.
- For more information about TRULICITY Single-Dose Pen, visit our website at: www.trulicity.com.

Scan this code to launch
www.trulicity.com

This Instructions for Use has been approved by the U.S. Food and Drug Administration.

Eli Lilly and Company
Indianapolis, IN 46285, USA
US License Number 1891
TRULICITY is a registered trademark of Eli Lilly and Company.

Copyright © 2020, 2023, Eli Lilly and Company. All rights reserved.

The TRULICITY Pen meets the current dose accuracy and functional requirements of ISO 11608-1:2012 and 11608-5:2012.

Implemented: 04/2023

TRU3MG-0002-IFU-20230407

TRULICITY 4.5 MG SINGLE-DOSE PEN INSTRUCTIONS FOR USE

Instructions for Use

TRULICITY® (TRU-li-si-tee)
(dulaglutide)
injection, for subcutaneous use
4.5 mg/0.5 mL Single-Dose Pen
use 1 time each week (once weekly)

Information About TRULICITY Single-Dose Pen

Please read this Instructions for Use and the Medication Guide carefully and completely before using your TRULICITY Single-Dose Pen. Talk to your healthcare provider about how to inject TRULICITY the right way.

- TRULICITY Single-Dose Pen (Pen) is a disposable, prefilled medicine delivery device. Each Pen contains 1 dose of TRULICITY (4.5 mg/0.5 mL). Each Pen should only be used 1 time.
- TRULICITY is used 1 time each week. You may want to mark your calendar to remind you when to take your next dose.

Before You Get Started

Remove

Check

Inspect

Prepare

Remove the Pen from the refrigerator.
Leave the Base Cap on until you are ready to inject.

Check the Pen label to make sure you have the right medicine and it has not expired.
Expiration Date

Check the Pen to make sure that it is not damaged and inspect the medicine to make sure it is not cloudy, discolored or has particles in it.

Wash your hands.

Choose Your Injection Site

Your healthcare provider can help you choose the injection site that is best for you.

Change (rotate) your injection site each week. You may use the same area of your body, but be sure to choose a different injection site in that area.
You may inject the medicine into your stomach (abdomen) or thigh.

Another person should give you the injection in the back of your upper arm.

Step 1 Uncap the Pen
Make sure the Pen is locked.

- Pull the Base Cap straight off and throw it away in your household trash.
  Do not put the Base Cap back on — this could damage the needle.
  Do not touch the needle.

Step 2 Place and Unlock

- Place the Clear Base flat and firmly against your skin at the injection site .

Unlock by turning the Lock Ring.

Step 3 Press and Hold

- Press and hold the green Injection Button. You will hear a loud click.
  Continue holding the Clear Base firmly against your skin until you hear a second click. This happens when the needle starts retracting in about 5-10 seconds.
- Remove the Pen from your skin.

Important Information

Disposal of Pen

Storage and Handling

Commonly Asked Questions

Other Information

Where to Learn More

Disposing of Your Used Pens

- Put your used Pens in a FDA-cleared sharps disposal container right away after use. Do not throw away (dispose of) Pens in your household trash.
- If you do not have a FDA-cleared sharps disposal container, you may use a household container that is:
  - made of a heavy-duty plastic,
  - can be closed with a tight-fitting, puncture-resistant lid, without sharps being able to come out,
  - upright and stable during use,
  - leak-resistant, and
  - properly labeled to warn of hazardous waste inside the container.
- When your sharps disposal container is almost full, you will need to follow your community guidelines for the right way to dispose of your sharps disposal container. There may be state or local laws about how you should throw away used needles and syringes. For more information about safe sharps disposal, and for specific information about sharps disposal in the state that you live in, go to the FDA's website at: http://www.fda.gov/safesharpsdisposal.
- Do not recycle your used sharps disposal container.

Storage and Handling

- Store your Pen in the refrigerator between 36°F to 46°F (2°C to 8°C).
- You may store your Pen at room temperature below 86°F (30°C) for a total of 14 days.
- Do not freeze your Pen. If the Pen has been frozen, throw the Pen away and use a new Pen.
- Storage of your Pen in the original carton is recommended. Protect your Pen from direct heat and light.
- The Pen has glass parts. Handle it carefully. If you drop it on a hard surface, do not use it. Use a new Pen for your injection.
- Keep your TRULICITY Pen and all medicines out of the reach of children.

Commonly Asked Questions

What if I see air bubbles in my Pen?

Air bubbles are normal.

What if I unlock the Pen and press the green Injection Button before pulling off the Base Cap?

Do not remove the Base Cap. Throw away the Pen and get a new Pen.

What if there is a drop of liquid on the tip of the needle when I remove the Base Cap?

A drop of liquid on the tip of the needle is normal.

Do I need to hold the Injection Button down until the injection is complete?

This is not necessary, but it may help you keep the Pen steady and firm against your skin.

I heard more than 2 clicks during my injection—2 louder clicks and 1 soft one. Did I get my complete injection?

Some people may hear a soft click right before the second loud click. That is the normal operation of the Pen. Do not remove the Pen from your skin until you hear the second louder click.

What if there is a drop of liquid or blood on my skin after my injection?

This is normal.

I am not sure if my Pen worked the right way.

Check to see if you have received your dose. Your dose was delivered the right way if the gray plunger is visible (see step 3). Also contact Lilly at 1-800-Lilly-Rx (1-800-545-5979) for further instructions. Until then, store your Pen safely to avoid an accidental needle stick.

Other Information

- If you have vision problems, do not use your Pen without help from a person trained to use the TRULICITY Pen.

Where to Learn More

- If you have any questions or problems with your TRULICITY Single-Dose Pen, contact Lilly at 1-800-Lilly-Rx (1-800-545-5979) or call your healthcare provider.
- For more information about TRULICITY Single-Dose Pen, visit our website at: www.trulicity.com.

Scan this code to launch
www.trulicity.com

This Instructions for Use has been approved by the U.S. Food and Drug Administration.
Eli Lilly and Company
Indianapolis, IN 46285, USA
US License Number 1891
TRULICITY is a registered trademark of Eli Lilly and Company.

Copyright © 2020, 2023, Eli Lilly and Company. All rights reserved.

The TRULICITY Pen meets the current dose accuracy and functional requirements of ISO 11608-1:2012 and 11608-5:2012.

Implemented: 04/2023

TRU4.5MG-0002-IFU-20230407

PACKAGE LABEL – Trulicity®, 0.75 mg/0.5 mL, Single-Dose Pens

NDC 0002-1433-80

4 Single-Dose Pens

Each pen delivers a 0.75 mg dose.

Use one pen every week.

Rx only

For subcutaneous use only

Single-Dose Only

Dispense the accompanying Medication Guide to each patient.

www.trulicity.com

trulilcity®

(dulaglutide) injection

0.75 mg/0.5 mL

once weekly

Lilly

PACKAGE LABEL – Trulicity®, 1.5 mg/0.5 mL, Single-Dose Pens

NDC 0002-1434-80

4 Single-Dose Pens

Each pen delivers a 1.5 mg dose.

Use one pen every week.

Rx only

For subcutaneous use only

Single-Dose Only

Dispense the accompanying Medication Guide to each patient.

www.trulicity.com

trulicity®

(dulaglutide) injection

1.5 mg/0.5 mL

once weekly

Lilly

PACKAGE LABEL – Trulicity®, 3 mg/0.5 mL, Single-Dose Pens

NDC 0002-2236-80

4 Single-Dose Pens

Each pen delivers a 3 mg dose.

Use one pen every week.

Rx only

For subcutaneous use only

Single-Dose Only

Dispense the accompanying Medication Guide to each patient.

www.trulicity.com

trulicity®

(dulaglutide) injection

3 mg/0.5 mL

once weekly

Lilly

PACKAGE LABEL – Trulicity®, 4.5 mg/0.5 mL, Single-Dose Pens

NDC 0002-3182-80

4 Single-Dose Pens

Each pen delivers a 4.5 mg dose.

Use one pen every week.

Rx only

For subcutaneous use only

Single-Dose Only

Dispense the accompanying Medication Guide to each patient.

www.trulicity.com

trulicity®

(dulaglutide) injection

4.5 mg/0.5 mL

once weekly

Lilly